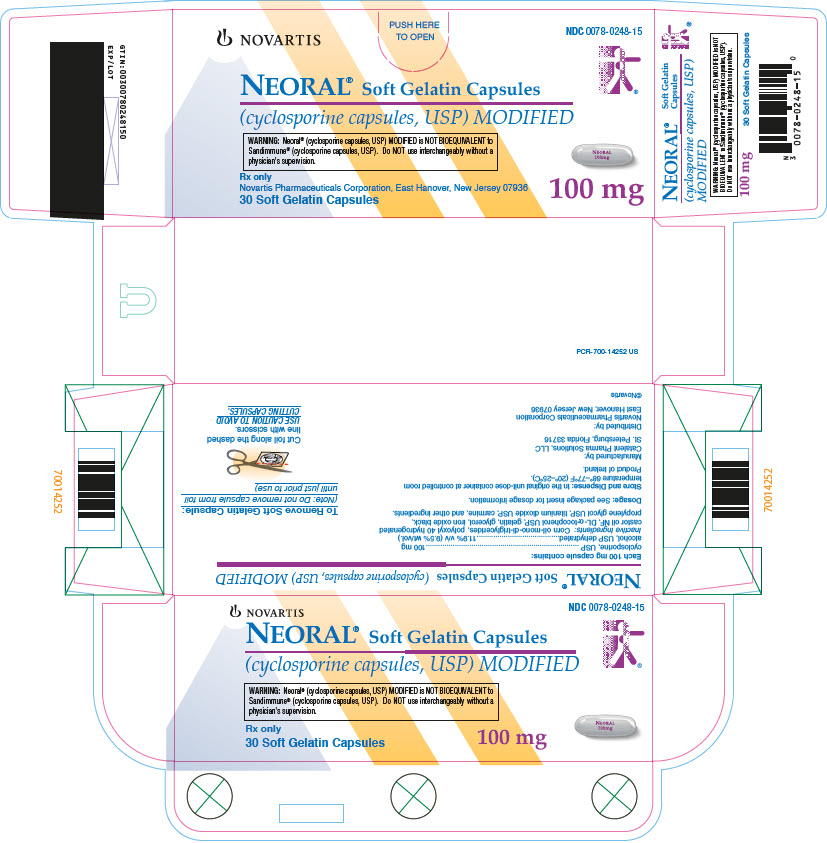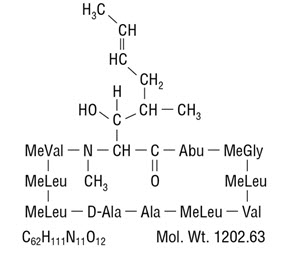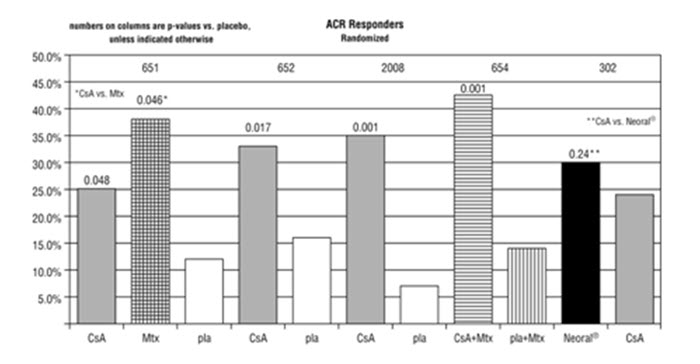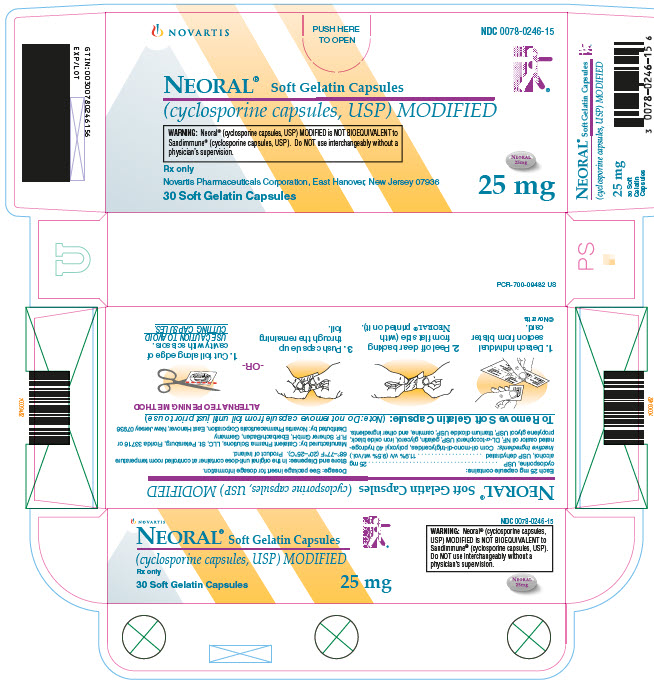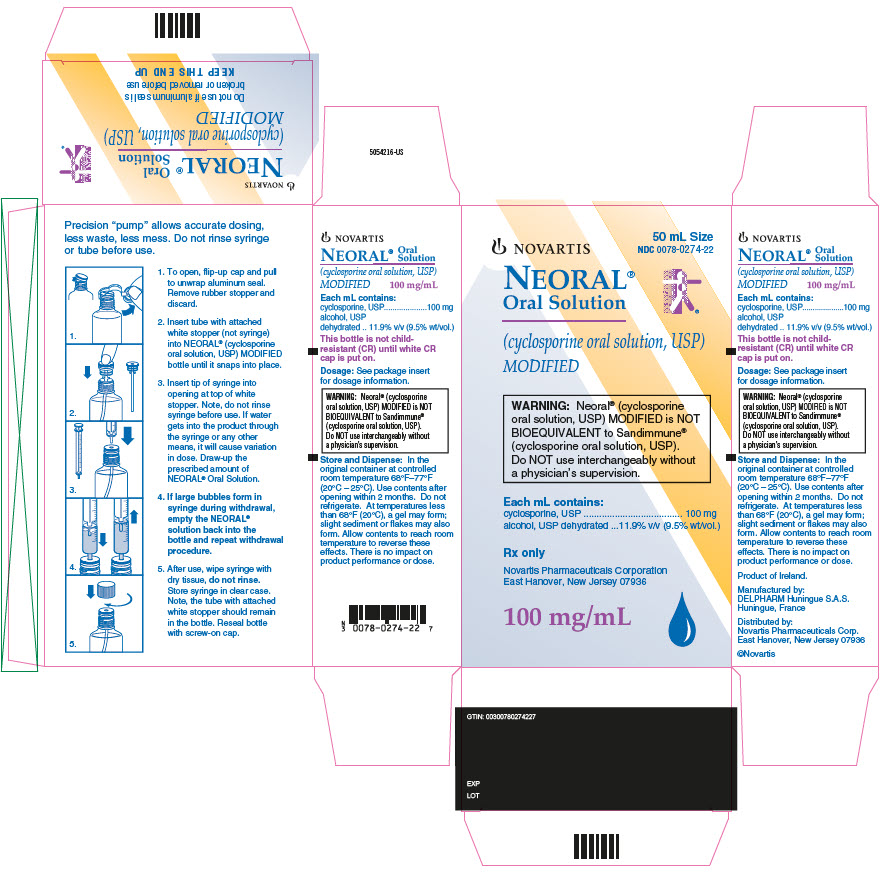 DRUG LABEL: Neoral
NDC: 0078-0246 | Form: CAPSULE, LIQUID FILLED
Manufacturer: Novartis Pharmaceuticals Corporation
Category: prescription | Type: HUMAN PRESCRIPTION DRUG LABEL
Date: 20251222

ACTIVE INGREDIENTS: CYCLOSPORINE 25 mg/1 1
INACTIVE INGREDIENTS: CORN OIL; POLYOXYL 40 HYDROGENATED CASTOR OIL; TOCOPHEROL; GELATIN; GLYCERIN; FERROSOFERRIC OXIDE; PROPYLENE GLYCOL; TITANIUM DIOXIDE; COCHINEAL

NEORAL® Soft Gelatin Capsules (cyclosporine capsules, USP) MODIFIED
NEORAL® Oral Solution (cyclosporine oral solution, USP) MODIFIED
Rx only
Prescribing Information

WARNING

Only physicians experienced in management of systemic immunosuppressive therapy for the indicated disease should prescribe Neoral. At doses used in solid organ transplantation, only physicians experienced in immunosuppressive therapy and management of organ transplant recipients should prescribe Neoral. Patients receiving the drug should be managed in facilities equipped and staffed with adequate laboratory and supportive medical resources. The physician responsible for maintenance therapy should have complete information requisite for the follow-up of the patient.

Neoral, a systemic immunosuppressant, may increase the susceptibility to infection and the development of neoplasia. In kidney, liver, and heart transplant patients Neoral may be administered with other immunosuppressive agents. Increased susceptibility to infection and the possible development of lymphoma and other neoplasms may result from the increase in the degree of immunosuppression in transplant patients.

Neoral Soft Gelatin Capsules (cyclosporine capsules, USP) MODIFIED and Neoral Oral Solution (cyclosporine oral solution, USP) MODIFIED have increased bioavailability in comparison to Sandimmune Soft Gelatin Capsules (cyclosporine capsules, USP) and Sandimmune Oral Solution (cyclosporine oral solution, USP). Neoral and Sandimmune are not bioequivalent and cannot be used interchangeably without physician supervision. For a given trough concentration, cyclosporine exposure will be greater with Neoral than with Sandimmune. If a patient who is receiving exceptionally high doses of Sandimmune is converted to Neoral, particular caution should be exercised. Cyclosporine blood concentrations should be monitored in transplant and rheumatoid arthritis patients taking Neoral to avoid toxicity due to high concentrations. Dose adjustments should be made in transplant patients to minimize possible organ rejection due to low concentrations. Comparison of blood concentrations in the published literature with blood concentrations obtained using current assays must be done with detailed knowledge of the assay methods employed (see DOSAGE AND ADMINISTRATION).

For Psoriasis Patients (see also BOXED WARNING above)

Psoriasis patients previously treated with PUVA and to a lesser extent, methotrexate or other immunosuppressive agents, UVB, coal tar, or radiation therapy, are at an increased risk of developing skin malignancies when taking Neoral.

Cyclosporine, the active ingredient in Neoral, in recommended dosages, can cause systemic hypertension and nephrotoxicity. The risk increases with increasing dose and duration of cyclosporine therapy. Renal dysfunction, including structural kidney damage, is a potential consequence of cyclosporine, and therefore, renal function must be monitored during therapy.

DESCRIPTION

Neoral is an oral formulation of cyclosporine that immediately forms a microemulsion in an aqueous environment.

Cyclosporine, the active principle in Neoral, is a cyclic polypeptide immunosuppressant agent consisting of 11 amino acids. It is produced as a metabolite by the fungus species Beauveria nivea.

Chemically, cyclosporine is designated as [R-[R*,R*-(E)]]-cyclic-(L-alanyl-D-alanyl-N-methyl-L-leucyl-N-methyl-L-leucyl-N-methyl-L-valyl-3-hydroxy-N,4-dimethyl-L-2-amino-6-octenoyl-L-α -amino-butyryl-N-methylglycyl-N-methyl-L-leucyl-L-valyl-N-methyl-L-leucyl).

Neoral Soft Gelatin Capsules

(cyclosporine capsules, USP) MODIFIED are available in 25 mg and 100 mg strengths.

Each 25 mg capsule contains:

cyclosporine………………………………………………………………………………25 mg

alcohol, USP dehydrated......................................................................11.9% v/v (9.5% wt/vol.)

Each 100 mg capsule contains:

cyclosporine……………………………………………………………………………...100 mg

alcohol, USP dehydrated.......................................................................11.9% v/v (9.5% wt/vol.)

Inactive ingredients: Carmine, corn oil-mono-di-triglycerides, DL-α-tocopherol USP, gelatin NF, glycerol, iron oxide black, polyoxyl 40 hydrogenated castor oil NF, propylene glycol USP, titanium dioxide USP, and other ingredients.

Neoral Oral Solution

(cyclosporine oral solution, USP) MODIFIED is available in 50 mL bottles.

Each mL contains:

cyclosporine……………………...............................................................................100 mg/mL

alcohol, USP dehydrated.....................................................................11.9% v/v (9.5% wt/vol.)

Inactive ingredients: Corn oil-mono-di-triglycerides, DL-α -tocopherol USP, polyoxyl 40 hydrogenated castor oil NF, and propylene glycol USP.

The chemical structure of cyclosporine (also known as cyclosporin A) is:

CLINICAL PHARMACOLOGY

Cyclosporine is a potent immunosuppressive agent that in animals prolongs survival of allogeneic transplants involving skin, kidney, liver, heart, pancreas, bone marrow, small intestine, and lung. Cyclosporine has been demonstrated to suppress some humoral immunity and to a greater extent, cell-mediated immune reactions such as allograft rejection, delayed hypersensitivity, experimental allergic encephalomyelitis, Freund’s adjuvant arthritis, and graft versus host disease in many animal species for a variety of organs.

The effectiveness of cyclosporine results from specific and reversible inhibition of immunocompetent lymphocytes in the G0- and G1-phase of the cell cycle. T-lymphocytes are preferentially inhibited. The T-helper cell is the main target, although the T-suppressor cell may also be suppressed. Cyclosporine also inhibits lymphokine production and release, including interleukin-2.

No effects on phagocytic function (changes in enzyme secretions, chemotactic migration of granulocytes, macrophage migration, carbon clearance in vivo) have been detected in animals. Cyclosporine does not cause bone marrow suppression in animal models or man.

Pharmacokinetics

The immunosuppressive activity of cyclosporine is primarily due to parent drug. Following oral administration, absorption of cyclosporine is incomplete. The extent of absorption of cyclosporine is dependent on the individual patient, the patient population, and the formulation. Elimination of cyclosporine is primarily biliary with only 6% of the dose (parent drug and metabolites) excreted in urine. The disposition of cyclosporine from blood is generally biphasic, with a terminal half-life of approximately 8.4 hours (range, 5 to 18 hours). Following intravenous administration, the blood clearance of cyclosporine (assay: HPLC) is approximately 5 to 7 mL/min/kg in adult recipients of renal or liver allografts. Blood cyclosporine clearance appears to be slightly slower in cardiac transplant patients.

The Neoral Soft Gelatin Capsules (cyclosporine capsules, USP) MODIFIED and Neoral Oral Solution (cyclosporine oral solution, USP) MODIFIED are bioequivalent. Neoral Oral Solution diluted with orange juice or apple juice is bioequivalent to Neoral Oral Solution diluted with water. The effect of milk on the bioavailability of cyclosporine when administered as Neoral Oral Solution has not been evaluated.

The relationship between administered dose and exposure (area under the concentration versus time curve, AUC) is linear within the therapeutic dose range. The intersubject variability (total, %CV) of cyclosporine exposure (AUC) when Neoral or Sandimmune is administered ranges from approximately 20% to 50% in renal transplant patients. This intersubject variability contributes to the need for individualization of the dosing regimen for optimal therapy (see DOSAGE AND ADMINISTRATION). Intrasubject variability of AUC in renal transplant recipients (%CV) was 9% to 21% for Neoral and 19% to 26% for Sandimmune. In the same studies, intrasubject variability of trough concentrations (%CV) was 17% to 30% for Neoral and 16% to 38% for Sandimmune.

Absorption

Neoral has increased bioavailability compared to Sandimmune. The absolute bioavailability of cyclosporine administered as Sandimmune is dependent on the patient population, estimated to be less than 10% in liver transplant patients and as great as 89% in some renal transplant patients. The absolute bioavailability of cyclosporine administered as Neoral has not been determined in adults. In studies of renal transplant, rheumatoid arthritis and psoriasis patients, the mean cyclosporine AUC was approximately 20% to 50% greater and the peak blood cyclosporine concentration (Cmax) was approximately 40% to 106% greater following administration of Neoral compared to following administration of Sandimmune. The dose normalized AUC in de novo liver transplant patients administered Neoral 28 days after transplantation was 50% greater and Cmax was 90% greater than in those patients administered Sandimmune. AUC and Cmax are also increased (Neoral relative to Sandimmune) in heart transplant patients, but data are very limited. Although the AUC and Cmax values are higher on Neoral relative to Sandimmune, the predose trough concentrations (dose-normalized) are similar for the two formulations.

Following oral administration of Neoral, the time to peak blood cyclosporine concentrations (Tmax) ranged from 1.5 to 2.0 hours. The administration of food with Neoral decreases the cyclosporine AUC and Cmax. A high fat meal (669 kcal, 45 grams fat) consumed within one-half hour before Neoral administration decreased the AUC by 13% and Cmax by 33%. The effects of a low-fat meal (667 kcal, 15 grams fat) were similar.

The effect of T-tube diversion of bile on the absorption of cyclosporine from Neoral was investigated in eleven de novo liver transplant patients. When the patients were administered Neoral with and without T-tube diversion of bile, very little difference in absorption was observed, as measured by the change in maximal cyclosporine blood concentrations from pre-dose values with the T-tube closed relative to when it was open: 6.9 ± 41% (range, 55% to 68%).

Pharmacokinetic Parameters (mean ± SD)
 | Dose/day^1 | Dose/weight | AUC^2 | Cmax | Trough^3 | CL/F | CL/F
Patient Population | (mg/d) | (mg/kg/d) | (ng·hr/mL) | (ng/mL) | (ng/mL) | (mL/min) | (mL/min/kg)
De novo renal transplant^4 | 597 ± 174 | 7.95 ± 2.81 | 8772 ± 2089 | 1802 ± 428 | 361 ± 129 | 593 ± 204 | 7.8 ± 2.9
Week 4 (N = 37)
Stable renal transplant^4 | 344 ± 122 | 4.10 ± 1.58 | 6035 ± 2194 | 1333 ± 469 | 251 ± 116 | 492 ± 140 | 5.9 ± 2.1
(N = 55)
De novo liver transplant^5 | 458 ± 190 | 6.89 ± 3.68 | 7187 ± 2816 | 1555 ± 740 | 268 ± 101 | 577 ± 309 | 8.6 ± 5.7
Week 4 (N = 18)
De novo rheumatoid arthritis^6 | 182 ± 55.6 | 2.37 ± 0.36 | 2641 ± 877 | 728 ± 263 | 96.4 ± 37.7 | 613 ± 196 | 8.3 ± 2.8
(N = 23)
De novo psoriasis^6 | 189 ± 69.8 | 2.48 ± 0.65 | 2324 ± 1048 | 655 ± 186 | 74.9 ± 46.7 | 723 ± 186 | 10.2 ± 3.9
Week 4 (N = 18)
^1Total daily dose was divided into two doses administered every 12 hours.
^2AUC was measured over one dosing interval.
^3Trough concentration was measured just prior to the morning Neoral dose, approximately 12 hours after the previous dose.
^4Assay: TDx specific monoclonal fluorescence polarization immunoassay.
^5Assay: Cyclo-trac specific monoclonal radioimmunoassay.
^6Assay: INCSTAR specific monoclonal radioimmunoassay.

Distribution

Cyclosporine is distributed largely outside the blood volume. The steady state volume of distribution during intravenous dosing has been reported as 3 to 5 L/kg in solid organ transplant recipients. In blood, the distribution is concentration dependent. Approximately 33% to 47% is in plasma, 4% to 9% in lymphocytes, 5% to 12% in granulocytes, and 41% to 58% in erythrocytes. At high concentrations, the binding capacity of leukocytes and erythrocytes becomes saturated. In plasma, approximately 90% is bound to proteins, primarily lipoproteins. Cyclosporine is excreted in human milk (see PRECAUTIONS, Nursing Mothers).

Metabolism

Cyclosporine is extensively metabolized by the cytochrome P-450 3A enzyme system in the liver, and to a lesser degree in the gastrointestinal tract, and the kidney. The metabolism of cyclosporine can be altered by the coadministration of a variety of agents (see PRECAUTIONS, Drug Interactions). At least 25 metabolites have been identified from human bile, feces, blood, and urine. The biological activity of the metabolites and their contributions to toxicity are considerably less than those of the parent compound. The major metabolites (M1, M9, and M4N) result from oxidation at the 1-beta, 9-gamma, and 4-N-demethylated positions, respectively. At steady state following the oral administration of Sandimmune, the mean AUCs for blood concentrations of M1, M9, and M4N are about 70%, 21%, and 7.5% of the AUC for blood cyclosporine concentrations, respectively. Based on blood concentration data from stable renal transplant patients (13 patients administered Neoral and Sandimmune in a crossover study), and bile concentration data from de novo liver transplant patients (4 administered Neoral, 3 administered Sandimmune), the percentage of dose present as M1, M9, and M4N metabolites is similar when either Neoral or Sandimmune is administered.

Excretion

Only 0.1% of a cyclosporine dose is excreted unchanged in the urine. Elimination is primarily biliary with only 6% of the dose (parent drug and metabolites) excreted in the urine. Neither dialysis nor renal failure alters cyclosporine clearance significantly.

Drug Interactions

When diclofenac or methotrexate was coadministered with cyclosporine in rheumatoid arthritis patients, the AUC of diclofenac and methotrexate, each was significantly increased (see PRECAUTIONS, Drug Interactions). No clinically significant pharmacokinetic interactions occurred between cyclosporine and aspirin, ketoprofen, piroxicam, or indomethacin.

Specific Populations

Renal Impairment

In a study performed in 4 subjects with end-stage renal disease (creatinine clearance < 5 mL/min), an intravenous infusion of 3.5 mg/kg of cyclosporine over 4 hours administered at the end of a hemodialysis session resulted in a mean volume of distribution (Vdss) of 3.49 L/kg and systemic clearance (CL) of 0.369 L/hr/kg. This systemic CL (0.369 L/hr/kg) was approximately two thirds of the mean systemic CL (0.56 L/hr/kg) of cyclosporine in historical control subjects with normal renal function. In 5 liver transplant patients, the mean clearance of cyclosporine on and off hemodialysis was 463 mL/min and 398 mL/min, respectively. Less than 1% of the dose of cyclosporine was recovered in the dialysate.

Hepatic Impairment

Cyclosporine is extensively metabolized by the liver. Since severe hepatic impairment may result in significantly increased cyclosporine exposures, the dosage of cyclosporine may need to be reduced in these patients.

Pediatric Population

Pharmacokinetic data from pediatric patients administered Neoral or Sandimmune are very limited. In 15 renal transplant patients aged 3-16 years, cyclosporine whole blood clearance after IV administration of Sandimmune was 10.6 ± 3.7 mL/min/kg (assay: Cyclo-trac specific RIA). In a study of 7 renal transplant patients aged 2 to 16, the cyclosporine clearance ranged from 9.8 to 15.5 mL/min/kg. In 9 liver transplant patients aged 0.6 to 5.6 years, clearance was 9.3 ± 5.4 mL/min/kg (assay: HPLC).

In the pediatric population, Neoral also demonstrates an increased bioavailability as compared to Sandimmune. In 7 liver de novo transplant patients aged 1.4 to 10 years, the absolute bioavailability of Neoral was 43% (range, 30% to 68%) and for Sandimmune, in the same individuals, absolute bioavailability was 28% (range, 17% to 42%).

Pediatric Pharmacokinetic Parameters (mean ± SD)
 | Dose/day | Dose/weight | AUC^1 | Cmax | CL/F | CL/F
Patient Population | (mg/d) | (mg/kg/d) | (ng·hr/mL) | (ng/mL) | (mL/min) | (mL/min/kg)
Stable liver transplant^2
Age 2-8, Dosed TID (N = 9) | 101 ± 25 | 5.95 ± 1.32 | 2163 ± 801 | 629 ± 219 | 285 ± 94 | 16.6 ± 4.3
Age 8-15, Dosed BID (N = 8) | 188 ± 55 | 4.96 ± 2.09 | 4272 ± 1462 | 975 ± 281 | 378 ± 80 | 10.2 ± 4.0
Stable liver transplant^3
Age 3, Dosed BID (N = 1) | 120 | 8.33 | 5832 | 1050 | 171 | 11.9
Age 8-15, Dosed BID (N = 5) | 158 ± 55 | 5.51 ± 1.91 | 4452 ± 2475 | 1013 ± 635 | 328 ± 121 | 11.0 ± 1.9
Stable renal transplant^3
Age 7-15, Dosed BID (N = 5) | 328 ± 83 | 7.37 ± 4.11 | 6922 ± 1988 | 1827 ± 487 | 418 ± 143 | 8.7 ± 2.9
^1AUC was measured over one dosing interval.
^2Assay: Cyclo-trac specific monoclonal radioimmunoassay.
^3Assay: TDx specific monoclonal fluorescence polarization immunoassay.

Geriatric Population

Comparison of single dose data from both normal elderly volunteers (N = 18, mean age 69 years) and elderly rheumatoid arthritis patients (N = 16, mean age 68 years) to single dose data in young adult volunteers (N = 16, mean age 26 years) showed no significant difference in the pharmacokinetic parameters.

CLINICAL TRIALS

Rheumatoid Arthritis

The effectiveness of Sandimmune and Neoral in the treatment of severe rheumatoid arthritis was evaluated in 5 clinical studies involving a total of 728 cyclosporine treated patients and 273 placebo treated patients.

A summary of the results is presented for the “responder” rates per treatment group, with a responder being defined as a patient having completed the trial with a 20% improvement in the tender and the swollen joint count and a 20% improvement in 2 of 4 of investigator global, patient global, disability, and erythrocyte sedimentation rates (ESR) for the Studies 651 and 652 and 3 of 5 of investigator global, patient global, disability, visual analog pain, and ESR for Studies 2008, 654 and 302.

Study 651 enrolled 264 patients with active rheumatoid arthritis with at least 20 involved joints, who had failed at least one major RA drug, using a 3:3:2 randomization to one of the following three groups: (1) cyclosporine dosed at 2.5 to 5 mg/kg/day, (2) methotrexate at 7.5 to 15 mg/week, or (3) placebo. Treatment duration was 24 weeks. The mean cyclosporine dose at the last visit was 3.1 mg/kg/day. See Graph below.

Study 652 enrolled 250 patients with active RA with > 6 active painful or tender joints who had failed at least one major RA drug. Patients were randomized using a 3:3:2 randomization to 1 of 3 treatment arms: (1) 1.5 to 5 mg/kg/day of cyclosporine, (2) 2.5 to 5 mg/kg/day of cyclosporine, and (3) placebo. Treatment duration was 16 weeks. The mean cyclosporine dose for group 2 at the last visit was 2.92 mg/kg/day. See Graph below.

Study 2008 enrolled 144 patients with active RA and > 6 active joints who had unsuccessful treatment courses of aspirin and gold or Penicillamine. Patients were randomized to 1 of 2 treatment groups (1) cyclosporine 2.5 to 5 mg/kg/day with adjustments after the first month to achieve a target trough level and (2) placebo. Treatment duration was 24 weeks. The mean cyclosporine dose at the last visit was 3.63 mg/kg/day. See Graph below.

Study 654 enrolled 148 patients who remained with active joint counts of 6 or more despite treatment with maximally tolerated methotrexate doses for at least three months. Patients continued to take their current dose of methotrexate and were randomized to receive, in addition, one of the following medications: (1) cyclosporine 2.5 mg/kg/day with dose increases of 0.5 mg/kg/day at weeks 2 and 4 if there was no evidence of toxicity and further increases of 0.5 mg/kg/day at weeks 8 and 16 if a < 30% decrease in active joint count occurred without any significant toxicity; dose decreases could be made at any time for toxicity or (2) placebo. Treatment duration was 24 weeks. The mean cyclosporine dose at the last visit was 2.8 mg/kg/day (range, 1.3 to 4.1). See Graph below.

Study 302 enrolled 299 patients with severe active RA, 99% of whom were unresponsive or intolerant to at least one prior major RA drug. Patients were randomized to 1 of 2 treatment groups (1) Neoral and (2) cyclosporine, both of which were started at 2.5 mg/kg/day and increased after 4 weeks for inefficacy in increments of 0.5 mg/kg/day to a maximum of 5 mg/kg/day and decreased at any time for toxicity. Treatment duration was 24 weeks. The mean cyclosporine dose at the last visit was 2.91 mg/kg/day (range, 0.72 to 5.17) for Neoral and 3.27 mg/kg/day (range, 0.73 to 5.68) for cyclosporine. See Graph below.

INDICATIONS AND USAGE

Kidney, Liver, and Heart Transplantation

Neoral is indicated for the prophylaxis of organ rejection in kidney, liver, and heart allogeneic transplants. Neoral has been used in combination with azathioprine and corticosteroids.

Rheumatoid Arthritis

Neoral is indicated for the treatment of patients with severe active, rheumatoid arthritis where the disease has not adequately responded to methotrexate. Neoral can be used in combination with methotrexate in rheumatoid arthritis patients who do not respond adequately to methotrexate alone.

Psoriasis

Neoral is indicated for the treatment of adult, nonimmunocompromised patients with severe (i.e., extensive and/or disabling), recalcitrant, plaque psoriasis who have failed to respond to at least one systemic therapy (e.g., PUVA, retinoids, or methotrexate) or in patients for whom other systemic therapies are contraindicated or cannot be tolerated.

While rebound rarely occurs, most patients will experience relapse with Neoral as with other therapies upon cessation of treatment.

CONTRAINDICATIONS

General

Neoral is contraindicated in patients with a hypersensitivity to cyclosporine or to any of the ingredients of the formulation.

Rheumatoid Arthritis

Rheumatoid arthritis patients with abnormal renal function, uncontrolled hypertension, or malignancies should not receive Neoral.

Psoriasis

Psoriasis patients who are treated with Neoral should not receive concomitant PUVA or UVB therapy, methotrexate or other immunosuppressive agents, coal tar or radiation therapy. Psoriasis patients with abnormal renal function, uncontrolled hypertension, or malignancies should not receive Neoral.

WARNINGS

(See also BOXED WARNING.)

All Patients

Cyclosporine, the active ingredient of Neoral, can cause nephrotoxicity and hepatotoxicity. The risk increases with increasing doses of cyclosporine. Renal dysfunction, including structural kidney damage, is a potential consequence of Neoral and therefore renal function must be monitored during therapy. Care should be taken in using cyclosporine with nephrotoxic drugs (see PRECAUTIONS).

Patients receiving Neoral require frequent monitoring of serum creatinine (see Special Monitoring under DOSAGE AND ADMINISTRATION). Elderly patients should be monitored with particular care, since decreases in renal function also occur with age. If patients are not properly monitored and doses are not properly adjusted, cyclosporine therapy can be associated with the occurrence of structural kidney damage and persistent renal dysfunction.

An increase in serum creatinine and BUN may occur during Neoral therapy and reflect a reduction in the glomerular filtration rate. Impaired renal function at any time requires close monitoring, and frequent dosage adjustment may be indicated. The frequency and severity of serum creatinine elevations increase with dose and duration of cyclosporine therapy. These elevations are likely to become more pronounced without dose reduction or discontinuation.

Because Neoral is not bioequivalent to Sandimmune, conversion from Neoral to Sandimmune using a 1:1 ratio (mg/kg/day) may result in lower cyclosporine blood concentrations. Conversion from Neoral to Sandimmune should be made with increased monitoring to avoid the potential of underdosing.

Kidney, Liver, and Heart Transplant

Nephrotoxicity

Cyclosporine, the active ingredient of Neoral, can cause nephrotoxicity and hepatotoxicity when used in high doses. It is not unusual for serum creatinine and BUN levels to be elevated during cyclosporine therapy. These elevations in renal transplant patients do not necessarily indicate rejection, and each patient must be fully evaluated before dosage adjustment is initiated.

Based on the historical Sandimmune experience with oral solution, nephrotoxicity associated with cyclosporine had been noted in 25% of cases of renal transplantation, 38% of cases of cardiac transplantation, and 37% of cases of liver transplantation. Mild nephrotoxicity was generally noted 2 to 3 months after renal transplant and consisted of an arrest in the fall of the pre-operative elevations of BUN and creatinine at a range of 35 to 45 mg/dL and 2.0 to 2.5 mg/dL, respectively. These elevations were often responsive to cyclosporine dosage reduction.

More overt nephrotoxicity was seen early after transplantation and was characterized by a rapidly rising BUN and creatinine. Since these events are similar to renal rejection episodes, care must be taken to differentiate between them. This form of nephrotoxicity is usually responsive to cyclosporine dosage reduction.

Although specific diagnostic criteria which reliably differentiate renal graft rejection from drug toxicity have not been found, a number of parameters have been significantly associated with one or the other. It should be noted however, that up to 20% of patients may have simultaneous nephrotoxicity and rejection.

Nephrotoxicity vs. Rejection
Parameter | Nephrotoxicity | Rejection
History | Donor > 50 years old or hypotensive Prolonged kidney preservation Prolonged anastomosis time Concomitant nephrotoxic drugs | Anti-donor immune response Retransplant patient
Clinical | Often > 6 weeks postopb Prolonged initial nonfunction (acute tubular necrosis) | Often < 4 weeks postopb Fever > 37.5°C Weight gain > 0.5 kg Graft swelling and tenderness Decrease in daily urine volume > 500 mL (or 50%)
Laboratory | CyA serum trough level > 200 ng/mL Gradual rise in Cr (< 0.15 mg/dL/day)a Cr plateau < 25% above baseline BUN/Cr ≥ 20 | CyA serum trough level < 150 ng/mL Rapid rise in Cr (> 0.3 mg/dL/day)a Cr > 25% above baseline BUN/Cr < 20
Biopsy | Arteriolopathy (medial hypertrophy a, hyalinosis, nodular deposits, intimal thickening, endothelial vacuolization, progressive scarring) Tubular atrophy, isometric vacuolization, isolated calcifications Minimal edema Mild focal infiltratesc Diffuse interstitial fibrosis, often striped form | Endovasculitisc (proliferationa, intimal arteritisb, necrosis, sclerosis) Tubulitis with RBCb and WBCb casts, some irregular vacuolization Interstitial edemac and hemorrhageb Diffuse moderate to severe mononuclear infiltratesd Glomerulitis (mononuclear cells)c
Aspiration Cytology | CyA deposits in tubular and endothelial cells Fine isometric vacuolization of tubular cells | Inflammatory infiltrate with mononuclear phagocytes, macrophages, lymphoblastoid cells, and activated T-cells These strongly express HLA-DR antigens
Urine Cytology | Tubular cells with vacuolization and granularization | Degenerative tubular cells, plasma cells, and lymphocyturia > 20% of sediment
Manometry Ultrasonography | Intracapsular pressure < 40 mm Hgb Unchanged graft cross sectional area | Intracapsular pressure > 40 mm Hgb Increase in graft cross sectional area AP diameter ≥ Transverse diameter
Magnetic Resonance Imagery | Normal appearance | Loss of distinct corticomedullary junction, swelling image intensity of parachyma approaching that of psoas, loss of hilar fat
Radionuclide Scan | Normal or generally decreased perfusion Decrease in tubular function (^131 I-hippuran) > decrease in perfusion (99m Tc DTPA) | Patchy arterial flow Decrease in perfusion > decrease in tubular function Increased uptake of Indium 111 labeled platelets or Tc-99m in colloid
Therapy | Responds to decreased cyclosporine | Responds to increased steroids or antilymphocyte globulin
ap < 0.05, bp < 0.01, cp < 0.001, dp < 0.0001

A form of a cyclosporine-associated nephropathy is characterized by serial deterioration in renal function and morphologic changes in the kidneys. From 5% to 15% of transplant recipients who have received cyclosporine will fail to show a reduction in rising serum creatinine despite a decrease or discontinuation of cyclosporine therapy. Renal biopsies from these patients will demonstrate one or several of the following alterations: tubular vacuolization, tubular microcalcifications, peritubular capillary congestion, arteriolopathy, and a striped form of interstitial fibrosis with tubular atrophy. Though none of these morphologic changes is entirely specific, a diagnosis of cyclosporine-associated structural nephrotoxicity requires evidence of these findings.

When considering the development of cyclosporine-associated nephropathy, it is noteworthy that several authors have reported an association between the appearance of interstitial fibrosis and higher cumulative doses or persistently high circulating trough concentrations of cyclosporine. This is particularly true during the first 6 post-transplant months when the dosage tends to be highest and when, in kidney recipients, the organ appears to be most vulnerable to the toxic effects of cyclosporine. Among other contributing factors to the development of interstitial fibrosis in these patients are prolonged perfusion time, warm ischemia time, as well as episodes of acute toxicity, and acute and chronic rejection. The reversibility of interstitial fibrosis and its correlation to renal function have not yet been determined. Reversibility of arteriolopathy has been reported after stopping cyclosporine or lowering the dosage.

Impaired renal function at any time requires close monitoring, and frequent dosage adjustment may be indicated.

In the event of severe and unremitting rejection, when rescue therapy with pulse steroids and monoclonal antibodies fail to reverse the rejection episode, it may be preferable to switch to alternative immunosuppressive therapy rather than increase the Neoral dose to excessive blood concentrations.

Due to the potential for additive or synergistic impairment of renal function, caution should be exercised when coadministering Neoral with other drugs that may impair renal function (see PRECAUTIONS, Drug Interactions).

Thrombotic Microangiopathy

Occasionally patients have developed a syndrome of thrombocytopenia and microangiopathic hemolytic anemia which may result in graft failure. The vasculopathy can occur in the absence of rejection and is accompanied by avid platelet consumption within the graft as demonstrated by Indium 111 labeled platelet studies. Neither the pathogenesis nor the management of this syndrome is clear. Though resolution has occurred after reduction or discontinuation of cyclosporine and 1) administration of streptokinase and heparin or 2) plasmapheresis, this appears to depend upon early detection with Indium 111 labeled platelet scans (see ADVERSE REACTIONS).

Hyperkalemia

Significant hyperkalemia (sometimes associated with hyperchloremic metabolic acidosis) and hyperuricemia have been seen occasionally in individual patients.

Hepatotoxicity

Cases of hepatotoxicity and liver injury, including cholestasis, jaundice, hepatitis, and liver failure, have been reported in patients treated with cyclosporine. Most reports included patients with significant co-morbidities, underlying conditions and other confounding factors including infectious complications and comedications with hepatotoxic potential. In some cases, mainly in transplant patients, fatal outcomes have been reported (see ADVERSE REACTIONS, Postmarketing Experience, Kidney, Liver and Heart Transplantation).

Hepatotoxicity, usually manifested by elevations in hepatic enzymes and bilirubin, was reported in patients treated with cyclosporine in clinical trials: 4% in renal transplantation, 7% in cardiac transplantation, and 4% in liver transplantation. This was usually noted during the first month of therapy when high doses of cyclosporine were used. The chemistry elevations usually decreased with a reduction in dosage.

Malignancies

As in patients receiving other immunosuppressants, those patients receiving cyclosporine are at increased risk for development of lymphomas and other malignancies, particularly those of the skin. Patients taking cyclosporine should be warned to avoid excess ultraviolet light exposure. The increased risk appears related to the intensity and duration of immunosuppression rather than to the use of specific agents. Because of the danger of oversuppression of the immune system resulting in increased risk of infection or malignancy, a treatment regimen containing multiple immunosuppressants should be used with caution. Some malignancies may be fatal. Transplant patients receiving cyclosporine are at increased risk for serious infection with fatal outcome.

Serious Infections

Patients receiving immunosuppressants, including Neoral, are at increased risk of developing bacterial, viral, fungal, and protozoal infections, including opportunistic infections. These infections may lead to serious, including fatal, outcomes (see BOXED WARNING, and ADVERSE REACTIONS).

Polyoma Virus Infections

Patients receiving immunosuppressants, including Neoral, are at increased risk for opportunistic infections, including polyoma virus infections. Polyoma virus infections in transplant patients may have serious, and sometimes, fatal outcomes. These include cases of JC virus-associated progressive multifocal leukoencephalopathy (PML), and polyoma virus-associated nephropathy (PVAN), especially due to BK virus infection, which have been observed in patients receiving cyclosporine. PVAN is associated with serious outcomes, including deteriorating renal function and renal graft loss, (see ADVERSE REACTIONS, Postmarketing Experience, Kidney, Liver and Heart Transplantation). Patient monitoring may help detect patients at risk for PVAN.

Cases of PML have been reported in patients treated with Neoral. PML, which is sometimes fatal, commonly presents with hemiparesis, apathy, confusion, cognitive deficiencies and ataxia. Risk factors for PML include treatment with immunosuppressant therapies and impairment of immune function. In immunosuppressed patients, physicians should consider PML in the differential diagnosis in patients reporting neurological symptoms and consultation with a neurologist should be considered as clinically indicated.

Consideration should be given to reducing the total immunosuppression in transplant patients who develop PML or PVAN. However, reduced immunosuppression may place the graft at risk.

Neurotoxicity

There have been reports of convulsions in adult and pediatric patients receiving cyclosporine, particularly in combination with high dose methylprednisolone.

Encephalopathy, including Posterior Reversible Encephalopathy Syndrome (PRES), has been described both in post-marketing reports and in the literature. Manifestations include impaired consciousness, convulsions, visual disturbances (including blindness), loss of motor function, movement disorders and psychiatric disturbances. In many cases, changes in the white matter have been detected using imaging techniques and pathologic specimens. Predisposing factors, such as hypertension, hypomagnesemia, hypocholesterolemia, high-dose corticosteroids, high cyclosporine blood concentrations, and graft-versus-host disease, have been noted in many but not all of the reported cases. The changes in most cases have been reversible upon discontinuation of cyclosporine, and in some cases improvement was noted after reduction of dose. It appears that patients receiving liver transplant are more susceptible to encephalopathy than those receiving kidney transplant. Another rare manifestation of cyclosporine-induced neurotoxicity, occurring in transplant patients more frequently than in other indications, is optic disc edema including papilloedema, with possible visual impairment, secondary to benign intracranial hypertension.

Care should be taken in using cyclosporine with nephrotoxic drugs (see PRECAUTIONS).

Rheumatoid Arthritis

Cyclosporine nephropathy was detected in renal biopsies of 6 out of 60 (10%) rheumatoid arthritis patients after the average treatment duration of 19 months. Only one patient, out of these 6 patients, was treated with a dose ≤ 4 mg/kg/day. Serum creatinine improved in all but one patient after discontinuation of cyclosporine. The “maximal creatinine increase” appears to be a factor in predicting cyclosporine nephropathy.

There is a potential, as with other immunosuppressive agents, for an increase in the occurrence of malignant lymphomas with cyclosporine. It is not clear whether the risk with cyclosporine is greater than that in rheumatoid arthritis patients or in rheumatoid arthritis patients on cytotoxic treatment for this indication. Five cases of lymphoma were detected: four in a survey of approximately 2,300 patients treated with cyclosporine for rheumatoid arthritis, and another case of lymphoma was reported in a clinical trial. Although other tumors (12 skin cancers, 24 solid tumors of diverse types, and 1 multiple myeloma) were also reported in this survey, epidemiologic analyses did not support a relationship to cyclosporine other than for malignant lymphomas.

Patients should be thoroughly evaluated before and during Neoral treatment for the development of malignancies. Moreover, use of Neoral therapy with other immunosuppressive agents may induce an excessive immunosuppression which is known to increase the risk of malignancy.

Psoriasis

(See also BOXED WARNING for Psoriasis.)

Since cyclosporine is a potent immunosuppressive agent with a number of potentially serious side effects, the risks and benefits of using Neoral should be considered before treatment of patients with psoriasis. Cyclosporine, the active ingredient in Neoral, can cause nephrotoxicity and hypertension (see PRECAUTIONS) and the risk increases with increasing dose and duration of therapy. Patients who may be at increased risk, such as those with abnormal renal function, uncontrolled hypertension or malignancies, should not receive Neoral.

Renal dysfunction is a potential consequence of Neoral therefore renal function must be monitored during therapy.

Patients receiving Neoral require frequent monitoring of serum creatinine (see Special Monitoring under DOSAGE AND ADMINISTRATION). Elderly patients should be monitored with particular care, since decreases in renal function also occur with age. If patients are not properly monitored and doses are not properly adjusted, cyclosporine therapy can cause structural kidney damage and persistent renal dysfunction.

An increase in serum creatinine and BUN may occur during Neoral therapy and reflects a reduction in the glomerular filtration rate.

Kidney biopsies from 86 psoriasis patients treated for a mean duration of 23 months with 1.2 to 7.6 mg/kg/day of cyclosporine showed evidence of cyclosporine nephropathy in 18/86 (21%) of the patients. The pathology consisted of renal tubular atrophy and interstitial fibrosis. On repeat biopsy of 13 of these patients maintained on various dosages of cyclosporine for a mean of 2 additional years, the number with cyclosporine induced nephropathy rose to 26/86 (30%). The majority of patients (19/26) were on a dose of ≥ 5.0 mg/kg/day (the highest recommended dose is 4 mg/kg/day). The patients were also on cyclosporine for greater than 15 months (18/26) and/or had a clinically significant increase in serum creatinine for greater than 1 month (21/26). Creatinine levels returned to normal range in 7 of 11 patients in whom cyclosporine therapy was discontinued.

There is an increased risk for the development of skin and lymphoproliferative malignancies in cyclosporine-treated psoriasis patients. The relative risk of malignancies is comparable to that observed in psoriasis patients treated with other immunosuppressive agents.

Tumors were reported in 32 (2.2%) of 1439 psoriasis patients treated with cyclosporine worldwide from clinical trials. Additional tumors have been reported in 7 patients in cyclosporine postmarketing experience. Skin malignancies were reported in 16 (1.1%) of these patients; all but 2 of them had previously received PUVA therapy. Methotrexate was received by 7 patients. UVB and coal tar had been used by 2 and 3 patients, respectively. Seven patients had either a history of previous skin cancer or a potentially predisposing lesion was present prior to cyclosporine exposure. Of the 16 patients with skin cancer, 11 patients had 18 squamous cell carcinomas and 7 patients had 10 basal cell carcinomas.

There were two lymphoproliferative malignancies; one case of non-Hodgkin’s lymphoma which required chemotherapy, and one case of mycosis fungoides which regressed spontaneously upon discontinuation of cyclosporine. There were four cases of benign lymphocytic infiltration: 3 regressed spontaneously upon discontinuation of cyclosporine, while the fourth regressed despite continuation of the drug. The remainder of the malignancies, 13 cases (0.9%), involved various organs.

Patients should not be treated concurrently with cyclosporine and PUVA or UVB, other radiation therapy, or other immunosuppressive agents, because of the possibility of excessive immunosuppression and the subsequent risk of malignancies (see CONTRAINDICATIONS). Patients should also be warned to protect themselves appropriately when in the sun, and to avoid excessive sun exposure. Patients should be thoroughly evaluated before and during treatment for the presence of malignancies remembering that malignant lesions may be hidden by psoriatic plaques. Skin lesions not typical of psoriasis should be biopsied before starting treatment. Patients should be treated with Neoral only after complete resolution of suspicious lesions, and only if there are no other treatment options (see Special Monitoring for Psoriasis Patients).

Special Excipients

Alcohol (ethanol)

The alcohol content (see DESCRIPTION) of Neoral should be taken into account when given to patients in whom alcohol intake should be avoided or minimized, e.g., pregnant or breastfeeding women, in patients presenting with liver disease or epilepsy, in alcoholic patients, or pediatric patients. For an adult weighing 70 kg, the maximum daily oral dose would deliver about 1 gram of alcohol (see DESCRIPTION for alcohol content of each formulation).

PRECAUTIONS

General

Hypertension

Cyclosporine is the active ingredient of Neoral. Hypertension is a common side effect of cyclosporine therapy which may persist (see ADVERSE REACTIONS and DOSAGE AND ADMINISTRATION for monitoring recommendations). Mild or moderate hypertension is encountered more frequently than severe hypertension and the incidence decreases over time. In recipients of kidney, liver, and heart allografts treated with cyclosporine, antihypertensive therapy may be required (see Special Monitoring of Rheumatoid Arthritis and Psoriasis Patients). However, since cyclosporine may cause hyperkalemia, potassium-sparing diuretics should not be used. While calcium antagonists can be effective agents in treating cyclosporine-associated hypertension, they can interfere with cyclosporine metabolism (see Drug Interactions).

Vaccination

During treatment with cyclosporine, vaccination may be less effective; and the use of live attenuated vaccines should be avoided.

Special Monitoring of Rheumatoid Arthritis Patients

Before initiating treatment, a careful physical examination, including blood pressure measurements (on at least two occasions) and two creatinine levels to estimate baseline should be performed. Blood pressure and serum creatinine should be evaluated every 2 weeks during the initial 3 months and then monthly if the patient is stable. It is advisable to monitor serum creatinine and blood pressure always after an increase of the dose of nonsteroidal anti-inflammatory drugs (NSAIDs) and after initiation of new NSAID therapy during Neoral treatment. If coadministered with methotrexate, CBC and liver function tests are recommended to be monitored monthly (see also PRECAUTIONS, General, Hypertension).

In patients who are receiving cyclosporine, the dose of Neoral should be decreased by 25% to 50% if hypertension occurs. If hypertension persists, the dose of Neoral should be further reduced or blood pressure should be controlled with antihypertensive agents. In most cases, blood pressure has returned to baseline when cyclosporine was discontinued.

In placebo-controlled trials of rheumatoid arthritis patients, systolic hypertension (defined as an occurrence of two systolic blood pressure readings > 140 mmHg) and diastolic hypertension (defined as two diastolic blood pressure readings > 90 mmHg) occurred in 33% and 19% of patients treated with cyclosporine, respectively. The corresponding placebo rates were 22% and 8%.

Special Monitoring for Psoriasis Patients

Before initiating treatment, a careful dermatological and physical examination, including blood pressure measurements (on at least two occasions) should be performed. Since Neoral is an immunosuppressive agent, patients should be evaluated for the presence of occult infection on their first physical examination and for the presence of tumors initially, and throughout treatment with Neoral. Skin lesions not typical for psoriasis should be biopsied before starting Neoral. Patients with malignant or premalignant changes of the skin should be treated with Neoral only after appropriate treatment of such lesions and if no other treatment option exists.

Baseline laboratories should include serum creatinine (on two occasions), BUN, CBC, serum magnesium, potassium, uric acid, and lipids.

The risk of cyclosporine nephropathy is reduced when the starting dose is low (2.5 mg/kg/day), the maximum dose does not exceed 4.0 mg/kg/day, serum creatinine is monitored regularly while cyclosporine is administered, and the dose of Neoral is decreased when the rise in creatinine is greater than or equal to 25% above the patient’s pretreatment level. The increase in creatinine is generally reversible upon timely decrease of the dose of Neoral or its discontinuation.

Serum creatinine and BUN should be evaluated every 2 weeks during the initial 3 months of therapy and then monthly if the patient is stable. If the serum creatinine is greater than or equal to 25% above the patient’s pretreatment level, serum creatinine should be repeated within two weeks. If the change in serum creatinine remains greater than or equal to 25% above baseline, Neoral should be reduced by 25% to 50%. If at any time the serum creatinine increases by greater than or equal to 50% above pretreatment level, Neoral should be reduced by 25% to 50%. Neoral should be discontinued if reversibility (within 25% of baseline) of serum creatinine is not achievable after two dosage modifications. It is advisable to monitor serum creatinine after an increase of the dose of nonsteroidal anti-inflammatory drug and after initiation of new nonsteroidal anti-inflammatory therapy during Neoral treatment.

Blood pressure should be evaluated every 2 weeks during the initial 3 months of therapy and then monthly if the patient is stable, or more frequently when dosage adjustments are made. Patients without a history of previous hypertension before initiation of treatment with Neoral, should have the drug reduced by 25% to 50% if found to have sustained hypertension. If the patient continues to be hypertensive despite multiple reductions of Neoral, then Neoral should be discontinued. For patients with treated hypertension, before the initiation of Neoral therapy, their medication should be adjusted to control hypertension while on Neoral. Neoral should be discontinued if a change in hypertension management is not effective or tolerable.

CBC, uric acid, potassium, lipids, and magnesium should also be monitored every 2 weeks for the first 3 months of therapy, and then monthly if the patient is stable or more frequently when dosage adjustments are made. Neoral dosage should be reduced by 25% to 50% for any abnormality of clinical concern.

In controlled trials of cyclosporine in psoriasis patients, cyclosporine blood concentrations did not correlate well with either improvement or with side effects such as renal dysfunction.

Information for Patients: Patients should be advised that any change of cyclosporine formulation should be made cautiously and only under physician supervision because it may result in the need for a change in dosage.

Patients should be informed of the necessity of repeated laboratory tests while they are receiving cyclosporine. Patients should be advised of the potential risks during pregnancy and informed of the increased risk of neoplasia. Patients should also be informed of the risk of hypertension and renal dysfunction.

Patients should be advised that during treatment with cyclosporine, vaccination may be less effective and the use of live attenuated vaccines should be avoided.

Patients should be given careful dosage instructions. Neoral Oral Solution (cyclosporine oral solution, USP) MODIFIED should be diluted, preferably with orange or apple juice that is at room temperature. The combination of Neoral Oral Solution (cyclosporine oral solution, USP) MODIFIED with milk can be unpalatable.

Patients should be advised to take Neoral on a consistent schedule with regard to time of day and relation to meals. Grapefruit and grapefruit juice affect metabolism, increasing blood concentration of cyclosporine, thus should be avoided.

Cyclosporine may impact the ability to drive and use machines. Patients should be advised to exercise care when driving or using machines if they experience neurological disturbances including confusion, somnolence, or dizziness and discuss with their healthcare provider (see WARNINGS and ADVERSE REACTIONS).

Laboratory Tests

In all patients treated with cyclosporine, renal and liver functions should be assessed repeatedly by measurement of serum creatinine, BUN, serum bilirubin, and liver enzymes. Serum lipids, magnesium, and potassium should also be monitored. Cyclosporine blood concentrations should be routinely monitored in transplant patients (see DOSAGE AND ADMINISTRATION, Blood Concentration Monitoring in Transplant Patients), and periodically monitored in rheumatoid arthritis patients.

Drug Interactions

A. Effect of Drugs and Other Agents on Cyclosporine Pharmacokinetics and/or Safety

All of the individual drugs cited below are well substantiated to interact with cyclosporine. In addition, concomitant use of NSAIDs with cyclosporine, particularly in the setting of dehydration, may potentiate renal dysfunction. Caution should be exercised when using other drugs which are known to impair renal function (see WARNINGS, Nephrotoxicity).

Drugs That May Potentiate Renal Dysfunction

Antibiotics | Antineoplastics | Antifungals | Anti-inflammatory Drugs | Gastrointestinal Agents | Immunosuppressives | Other Drugs
ciprofloxacin | melphalan | amphotericin B | azapropazon | cimetidine | tacrolimus | fibric acid derivatives (e.g., bezafibrate, fenofibrate)
gentamicin |  | ketoconazole | colchicine | ranitidine |  | methotrexate
tobramycin |  |  | diclofenac
trimethoprim with sulfamethoxazole |  |  | naproxen
vancomycin |  |  | sulindac

During the concomitant use of a drug that may exhibit additive or synergistic renal impairment with cyclosporine, close monitoring of renal function (in particular serum creatinine) should be performed. If a significant impairment of renal function occurs, the dosage of the coadministered drug should be reduced or an alternative treatment considered.

Cyclosporine is extensively metabolized by CYP 3A isoenzymes, in particular CYP3A4, and is a substrate of the multidrug efflux transporter P-glycoprotein. Various agents are known to either increase or decrease plasma or whole blood concentrations of cyclosporine usually by inhibition or induction of CYP3A4 or P-glycoprotein transporter or both. Compounds that decrease cyclosporine absorption, such as orlistat, should be avoided. Appropriate Neoral dosage adjustment to achieve the desired cyclosporine concentrations is essential when drugs that significantly alter cyclosporine concentrations are used concomitantly (see Blood Concentration Monitoring).

1. Drugs That Increase Cyclosporine Concentrations

Calcium Channel Blockers | Antifungals | Antibiotics | Glucocorticoids | Other Drugs
diltiazem | fluconazole | azithromycin | methylprednisolone | Allopurinol
nicardipine | itraconazole | clarithromycin |  | Amiodarone
verapamil | ketoconazole | erythromycin |  | Bromocriptine
 | voriconazole | quinupristin/ dalfopristin |  | colchicine
 |  |  |  | danazol
 |  |  |  | imatinib
 |  |  |  | metoclopramide
 |  |  |  | nefazodone
 |  |  |  | oral contraceptives

HIV Protease Inhibitors

The HIV protease inhibitors (e.g., indinavir, nelfinavir, ritonavir, and saquinavir) are known to inhibit cytochrome P-450 3A and thus could potentially increase the concentrations of cyclosporine, however no formal studies of the interaction are available. Care should be exercised when these drugs are administered concomitantly.

Grapefruit Juice

Grapefruit and grapefruit juice affect metabolism, increasing blood concentrations of cyclosporine, thus should be avoided.

2. Drugs/Dietary Supplements That Decrease Cyclosporine Concentrations

Antibiotics | Anticonvulsants | Other Drugs/Dietary Supplements
nafcillin | carbamazepine | bosentan | St. John’s Wort
rifampin | oxcarbazepine | octreotide
 | phenobarbital | orlistat
 | phenytoin | sulfinpyrazone
 |  | terbinafine
 |  | ticlopidine

Bosentan

Coadministration of bosentan (250 to 1000 mg every 12 hours based on tolerability) and cyclosporine (300 mg every 12 hours for 2 days then dosing to achieve a Cmin of 200 to 250 ng/mL) for 7 days in healthy subjects resulted in decreases in the cyclosporine mean dose-normalized AUC, Cmax, and trough concentration of approximately 50%, 30%, and 60%, respectively, compared to when cyclosporine was given alone (see Effect of Cyclosporine on the Pharmacokinetics and/or Safety of Other Drugs or Agents). Coadministration of cyclosporine with bosentan should be avoided.

Boceprevir

Coadministration of boceprevir (800 mg three times daily for 7 days) and cyclosporine (100 mg single dose) in healthy subjects resulted in increases in the mean AUC and Cmax of cyclosporine approximately 2.7-fold and 2-fold, respectively, compared to when cyclosporine was given alone.

Telaprevir

Coadministration of telaprevir (750 mg every 8 hours for 11 days) with cyclosporine (10 mg on day 8) in healthy subjects resulted in increases in the mean dose-normalized AUC and Cmax of cyclosporine approximately 4.5-fold and 1.3-fold, respectively, compared to when cyclosporine (100 mg single dose) was given alone.

St. John’s Wort

There have been reports of a serious drug interaction between cyclosporine and the herbal dietary supplement St. John’s Wort. This interaction has been reported to produce a marked reduction in the blood concentrations of cyclosporine, resulting in subtherapeutic levels, rejection of transplanted organs, and graft loss.

Rifabutin

Rifabutin is known to increase the metabolism of other drugs metabolized by the cytochrome P-450 system. The interaction between rifabutin and cyclosporine has not been studied. Care should be exercised when these two drugs are administered concomitantly.

B. Effect of Cyclosporine on the Pharmacokinetics and/or Safety of Other Drugs or Agents

Cyclosporine is an inhibitor of CYP3A4 and of multiple drug efflux transporters (e.g., P-glycoprotein) and may increase plasma concentrations of comedications that are substrates of CYP3A4, P-glycoprotein or organic anion transporter proteins.

Cyclosporine may reduce the clearance of digoxin, colchicine, prednisolone, HMG-CoA reductase inhibitors (statins), aliskiren, bosentan, dabigatran, repaglinide, NSAIDs, sirolimus, etoposide, and other drugs.

See the full prescribing information of the other drug for further information and specific recommendations. The decision on coadministration of cyclosporine with other drugs or agents should be made by the healthcare provider following the careful assessment of benefits and risks.

Digoxin

Severe digitalis toxicity has been seen within days of starting cyclosporine in several patients taking digoxin. If digoxin is used concurrently with cyclosporine, serum digoxin concentrations should be monitored.

Colchicine

There are reports on the potential of cyclosporine to enhance the toxic effects of colchicine such as myopathy and neuropathy, especially in patients with renal dysfunction. Concomitant administration of cyclosporine and colchicine results in significant increases in colchicine plasma concentrations. If colchicine is used concurrently with cyclosporine, a reduction in the dosage of colchicine is recommended.

HMG-CoA Reductase Inhibitors (Statins)

Literature and postmarketing cases of myotoxicity, including muscle pain and weakness, myositis, and rhabdomyolysis, have been reported with concomitant administration of cyclosporine with lovastatin, simvastatin, atorvastatin, pravastatin, and rarely fluvastatin. When concurrently administered with cyclosporine, the dosage of these statins should be reduced according to label recommendations. Statin therapy needs to be temporarily withheld or discontinued in patients with signs and symptoms of myopathy or those with risk factors predisposing to severe renal injury, including renal failure, secondary to rhabdomyolysis.

Repaglinide

Cyclosporine may increase the plasma concentrations of repaglinide and thereby increase the risk of hypoglycemia. In 12 healthy male subjects who received two doses of 100 mg cyclosporine capsule orally 12 hours apart with a single dose of 0.25 mg repaglinide tablet (one-half of a 0.5 mg tablet) orally 13 hours after the cyclosporine initial dose, the repaglinide mean Cmax and AUC were increased 1.8-fold (range, 0.6 to 3.7-fold) and 2.4-fold (range, 1.2 to 5.3-fold), respectively. Close monitoring of blood glucose level is advisable for a patient taking cyclosporine and repaglinide concomitantly.

Ambrisentan

Coadministration of ambrisentan (5 mg daily) and cyclosporine (100 to 150 mg twice daily initially, then dosing to achieve Cmin 150 to 200 ng/mL) for 8 days in healthy subjects resulted in mean increases in ambrisentan AUC and Cmax of approximately 2-fold and 1.5–fold, respectively, compared to ambrisentan alone. When coadministering ambrisentan with cyclosporine, the ambrisentan dose should not be titrated to the recommended maximum daily dose.

Anthracycline Antibiotics

High doses of cyclosporine (e.g., at starting intravenous dose of 16 mg/kg/day) may increase the exposure to anthracycline antibiotics (e.g., doxorubicin, mitoxantrone, daunorubicin) in cancer patients.

Aliskiren

Cyclosporine alters the pharmacokinetics of aliskiren, a substrate of P-glycoprotein and CYP3A4. In 14 healthy subjects who received concomitantly single doses of cyclosporine (200 mg) and reduced dose aliskiren (75 mg), the mean Cmax of aliskiren was increased by approximately 2.5-fold (90% CI: 1.96 to 3.17) and the mean AUC by approximately 4.3-fold (90% CI: 3.52 to 5.21), compared to when these subjects received aliskiren alone. The concomitant administration of aliskiren with cyclosporine prolonged the median aliskiren elimination half-life (26 hours versus 43 to 45 hours) and the Tmax (0.5 hours versus 1.5 to 2.0 hours). The mean AUC and Cmax of cyclosporine were comparable to reported literature values. Coadministration of cyclosporine and aliskiren in these subjects also resulted in an increase in the number and/or intensity of adverse events, mainly headache, hot flush, nausea, vomiting, and somnolence. The coadministration of cyclosporine with aliskiren is not recommended.

Bosentan

In healthy subjects, coadministration of bosentan and cyclosporine resulted in time-dependent mean increases in dose-normalized bosentan trough concentrations (i.e., approximately 21-fold on day 1 and 2-fold on day 8 (steady state)) compared to when bosentan was given alone as a single dose on day 1 (see Effect of Drugs and Other Agents on Cyclosporine Pharmacokinetics and/or Safety). Coadministration of cyclosporine with bosentan should be avoided.

Dabigatran

The effect of cyclosporine on dabigatran concentrations had not been formally studied. Concomitant administration of dabigatran and cyclosporine may result in increased plasma dabigatran concentrations due to the P-gp inhibitory activity of cyclosporine. Coadministration of cyclosporine with dabigatran should be avoided.

Potassium-Sparing Diuretics

Cyclosporine should not be used with potassium-sparing diuretics because hyperkalemia can occur. Caution is also required when cyclosporine is coadministered with potassium sparing drugs (e.g., angiotensin converting enzyme inhibitors, angiotensin II receptor antagonists), potassium-containing drugs as well as in patients on a potassium rich diet. Control of potassium levels in these situations is advisable.

Nonsteroidal Anti-inflammatory Drug (NSAID) Interactions

Clinical status and serum creatinine should be closely monitored when cyclosporine is used with NSAIDs in rheumatoid arthritis patients (see WARNINGS).

Pharmacodynamic interactions have been reported to occur between cyclosporine and both naproxen and sulindac, in that concomitant use is associated with additive decreases in renal function, as determined by 99mTc-diethylenetriaminepentaacetic acid (DTPA) and (p-aminohippuric acid) PAH clearances. Although concomitant administration of diclofenac does not affect blood concentrations of cyclosporine, it has been associated with approximate doubling of diclofenac blood concentrations and occasional reports of reversible decreases in renal function. Consequently, the dose of diclofenac should be in the lower end of the therapeutic range.

Methotrexate Interaction

Preliminary data indicate that when methotrexate and cyclosporine were coadministered to rheumatoid arthritis patients (N = 20), methotrexate concentrations (AUCs) were increased approximately 30% and the concentrations (AUCs) of its metabolite, 7-hydroxy methotrexate, were decreased by approximately 80%. The clinical significance of this interaction is not known. Cyclosporine concentrations do not appear to have been altered (N = 6).

Sirolimus

Elevations in serum creatinine were observed in studies using sirolimus in combination with full-dose cyclosporine. This effect is often reversible with cyclosporine dose reduction. Simultaneous coadministration of cyclosporine significantly increases blood levels of sirolimus. To minimize increases in sirolimus concentrations, it is recommended that sirolimus be given 4 hours after cyclosporine administration.

Nifedipine

Frequent gingival hyperplasia when nifedipine is given concurrently with cyclosporine has been reported. The concomitant use of nifedipine should be avoided in patients in whom gingival hyperplasia develops as a side effect of cyclosporine.

Methylprednisolone

Convulsions when high dose methylprednisolone is given concurrently with cyclosporine have been reported.

Other Immunosuppressive Drugs and Agents

Psoriasis patients receiving other immunosuppressive agents or radiation therapy (including PUVA and UVB) should not receive concurrent cyclosporine because of the possibility of excessive immunosuppression.

Interactions Resulting in Decrease of Other Drug Levels

Cyclosporine inhibits the enterohepatic circulation of mycophenolic acid (MPA). Concomitant administration of cyclosporine and mycophenolate mofetil or mycophenolate sodium in transplant patients may decrease the mean exposure of MPA by 20% - 50% when compared with other immunosuppressants, which could reduce efficacy of mycophenolate mofetil or mycophenolate sodium. Monitor patients for alterations in efficacy of mycophenolate mofetil or mycophenolate sodium, when they are coadministered with cyclosporine.

C. Effect of Cyclosporine on the Efficacy of Live Vaccines

During treatment with cyclosporine, vaccination may be less effective. The use of live vaccines should be avoided.

For additional information on Cyclosporine Drug Interactions please contact Novartis Medical Affairs Department at 1-888-NOW-NOVA (1-888-669-6682).

Carcinogenesis, Mutagenesis, and Impairment of Fertility

Carcinogenicity studies were carried out in male and female rats and mice. In the 78-week mouse study, evidence of a statistically significant trend was found for lymphocytic lymphomas in females, and the incidence of hepatocellular carcinomas in mid-dose [0.03 times the maximum recommended human dose (MRHD) based on body surface area (BSA) males significantly exceeded the control value. In the 24-month rat study, pancreatic islet cell adenomas significantly exceeded the control rate in the low dose level (0.006 times the MRHD based on BSA]. The hepatocellular carcinomas and pancreatic islet cell adenomas were not dose related. Published reports indicate that co-treatment of hairless mice with UV irradiation and cyclosporine or other immunosuppressive agents shorten the time to skin tumor formation compared to UV irradiation alone.

Cyclosporine has not been found to be mutagenic/genotoxic in the Ames Test, the V79-HGPRT Test, the micronucleus test in mice and Chinese hamsters, the chromosome-aberration tests in Chinese hamster bone-marrow, the mouse dominant lethal assay, and the DNA-repair test in sperm from treated mice. A recent study analyzing sister chromatid exchange (SCE) induction by cyclosporine using human lymphocytes in vitro gave indication of a positive effect (i.e., induction of SCE), at high concentrations in this system.

In a fertility study in rats, increased perinatal mortality and impaired postnatal development of F1 pups were observed at 15 mg/kg/day (0.2 times the MRHD based on BSA). No adverse effects on fertility and reproduction were observed up to 5 mg/kg/day (0.06 times the MRHD based on BSA) in male and female rats.

Widely distributed papillomatosis of the skin was observed after chronic treatment of dogs with cyclosporine at 9 times the human initial psoriasis treatment dose of 2.5 mg/kg, where doses are expressed on a body surface area basis. This papillomatosis showed a spontaneous regression upon discontinuation of cyclosporine.

An increased incidence of malignancy is a recognized complication of immunosuppression in recipients of organ transplants and patients with rheumatoid arthritis and psoriasis. The most common forms of neoplasms are non-Hodgkin’s lymphoma and carcinomas of the skin. The risk of malignancies in cyclosporine recipients is higher than in the normal, healthy population but similar to that in patients receiving other immunosuppressive therapies. Reduction or discontinuance of immunosuppression may cause the lesions to regress.

In psoriasis patients on cyclosporine, development of malignancies, especially those of the skin has been reported (see WARNINGS). Skin lesions not typical for psoriasis should be biopsied before starting cyclosporine treatment. Patients with malignant or premalignant changes of the skin should be treated with cyclosporine only after appropriate treatment of such lesions and if no other treatment option exists.

Pregnancy

Pregnancy Exposure Registry

There is a pregnancy exposure registry that monitors pregnancy outcomes in women exposed to cyclosporine, including Neoral, during pregnancy. Encourage women who are taking Neoral during pregnancy to enroll in the Transplant Pregnancy Registry International (TPRI) by calling 1-877-955-8677 or visiting https://www.transplantpregnancyregistry.org.

Risk Summary

Available data from published literature, including the Transplant Pregnancy Registry International, observational cohort studies, case-controlled studies, meta-analysis, case series, and case reports, over decades of use with cyclosporine in pregnancy have not identified a drug associated risk of major birth defects, or miscarriage. Adverse maternal or fetal outcomes including hypertension, preeclampsia, preterm birth, and low birth weight are increased in patients treated with cyclosporine. However, patients receiving cyclosporine during pregnancy have underlying medical conditions and may be treated with concomitant medications that limit the interpretability of these findings (see Data).

Embryo-fetal developmental (EFD) studies in rats and rabbits with cyclosporine have shown embryo-fetal toxicity at dose levels below the MRHD based on BSA.

The alcohol content of Neoral should be taken into account when given to pregnant women (see WARNINGS, Special Excipients).

The estimated background risk of major birth defects and miscarriage for the indicated populations is unknown. All pregnancies have a background risk of birth defect, loss, or other adverse outcomes. In the U.S. general population, the estimated background risk of major birth defects and miscarriage in clinically recognized pregnancies is 2% to 4% and 15% to 20%, respectively.

Data

Human Data

Available data from the National Transplantation Pregnancy Registry (NTPR) including 622 pregnancies in renal, liver, and heart transplant recipients exposed to cyclosporine during pregnancy found that the overall rate of major birth defects, live birth rates, and miscarriage rates were comparable to the general population. Maternal and fetal adverse outcomes, including the rate of hypertension, preeclampsia, premature births, and low birth weight infants appear to be increased in transplant recipients treated with cyclosporine compared to the general population. However, these patients have underlying medical conditions that confound the above findings.

Animal Data

Animal studies have shown reproductive toxicity in rats and rabbits.

Three EFD studies (two oral and one intravenous) are available in rats. In two EFD studies, pregnant rats were orally administered with cyclosporine either at doses of 10, 17, 30, 100 and 300 mg/kg/day or 4, 10 and 25 mg/kg/day from gestation day (GD) 6 to 15 or from GD 7 to 17, respectively. Maternal toxicity characterized by mortality, clinical signs of toxicity and impaired body weight gain were observed at 30 mg/kg/day and above. Cyclosporine was embryo- and fetotoxic as indicated by increased embryonic mortality and reduced fetal weight together with skeletal retardations in rats at 25 mg/kg/day and above. In addition, ventricular septal defect was observed at 25 mg/kg/day in fetuses. In the first study, the oral no observed effect level (NOEL) for both dams and fetuses was 17 mg/kg/day (0.2 times the MRHD based on BSA). In the other oral study, the NOEL for dams and fetuses were 10 and 4 mg/kg/day (0.13 and 0.05 times the MRHD based on BSA), respectively. In the IV EFD study, rats were administered with 3, 6 and 12 mg/kg/day of cyclosporine from GD 7 to 17. An increase in post implantation loss was observed at 12 mg/kg/day; ventricular septal defect was observed at ≥ 6 mg/kg/day in fetuses. The IV NOEL for dams and fetus were 6 and 3 mg/kg/day (0.08 and 0.04 times the MRHD, respectively, based on BSA), respectively, after IV administration.

In rabbits, cyclosporine was orally administered at dose levels of 10, 30, 100 or 300 mg/kg/day from GD 6 to 18. At 100 mg/kg/day and above, reduction in body weight gain of dams and at 300 mg/kg/day abortions were observed. Maternal toxicity, embryo-fetotoxicity as indicated by increased pre- and postnatal mortality, reduced fetal weight together with skeletal retardations were observed at 100 mg/kg/day and above. The NOEL for dams and fetuses was 30 mg/kg/day (1 times the MRHD based on BSA).

In two published research studies, rabbits exposed to cyclosporine in utero (10 mg/kg/day subcutaneously) demonstrated reduced numbers of nephrons, renal hypertrophy, systemic hypertension and progressive renal insufficiency up to 35 weeks of age. These findings have not been demonstrated in other species and their relevance for humans is unknown.

In a peri- and postnatal development study in rats, pregnant rats were orally administered with cyclosporine (5, 15 or 45 mg/kg/day) from GD 15 until end of lactation. At 45 mg/kg/day (0.5 times the MRHD based on BSA), increased pre and postnatal mortality of offspring and reduced body weight gain of surviving pups were observed. Cyclosporine up to 15 mg/kg/day (0.2 times the MRHD based on BSA) had no effect on pregnancy, pre and postnatal development of offspring.

Nursing Mothers

Risk Summary

Cyclosporine and its metabolites are present in human milk following oral and intravenous administration. Adverse effects on the breastfed infant have not been reported. There are no data on the effects of the drug on milk production. The alcohol content of Neoral should be taken into account when given to lactating women (see WARNINGS, Special Excipients). Lactating women are encouraged to avoid additional alcohol intake during treatment. The developmental and health benefits of breastfeeding should be considered along with the mother's clinical need for Neoral and any potential adverse effects on the breastfed infant from Neoral or from the underlying maternal condition.

Pediatric Use

Although no adequate and well-controlled studies have been completed in children, transplant recipients as young as one year of age have received Neoral with no unusual adverse effects. The safety and efficacy of Neoral treatment in children with juvenile rheumatoid arthritis or psoriasis below the age of 18 have not been established.

Geriatric Use

In rheumatoid arthritis clinical trials with cyclosporine, 17.5% of patients were age 65 or older. These patients were more likely to develop systolic hypertension on therapy, and more likely to show serum creatinine rises ≥ 50% above the baseline after 3 to 4 months of therapy.

Clinical studies of Neoral in transplant and psoriasis patients did not include a sufficient number of subjects aged 65 and over to determine whether they respond differently from younger subjects. Other reported clinical experiences have not identified differences in response between the elderly and younger patients. In general, dose selection for an elderly patient should be cautious, usually starting at the low end of the dosing range, reflecting the greater frequency of decreased hepatic, renal, or cardiac function, and of concomitant disease or other drug therapy.

ADVERSE REACTIONS

Kidney, Liver, and Heart Transplantation

The principal adverse reactions of cyclosporine therapy are renal dysfunction, tremor, hirsutism, hypertension, and gum hyperplasia.

Hypertension

Hypertension, which is usually mild to moderate, may occur in approximately 50% of patients following renal transplantation and in most cardiac transplant patients.

Glomerular Capillary Thrombosis

Glomerular capillary thrombosis has been found in patients treated with cyclosporine and may progress to graft failure. The pathologic changes resembled those seen in the hemolytic-uremic syndrome and included thrombosis of the renal microvasculature, with platelet-fibrin thrombi occluding glomerular capillaries and afferent arterioles, microangiopathic hemolytic anemia, thrombocytopenia, and decreased renal function. Similar findings have been observed when other immunosuppressives have been employed post-transplantation.

Hypomagnesemia

Hypomagnesemia has been reported in some, but not all, patients exhibiting convulsions while on cyclosporine therapy. Although magnesium-depletion studies in normal subjects suggest that hypomagnesemia is associated with neurologic disorders, multiple factors, including hypertension, high dose methylprednisolone, hypocholesterolemia, and nephrotoxicity associated with high plasma concentrations of cyclosporine appear to be related to the neurological manifestations of cyclosporine toxicity.

Clinical Studies

In controlled studies, the nature, severity, and incidence of the adverse events that were observed in 493 transplanted patients treated with Neoral were comparable with those observed in 208 transplanted patients who received Sandimmune in these same studies when the dosage of the two drugs was adjusted to achieve the same cyclosporine blood trough concentrations.

Based on the historical experience with Sandimmune, the following reactions occurred in 3% or greater of 892 patients involved in clinical trials of kidney, heart, and liver transplants.

 |  | Randomized Kidney Patients |  | Cyclosporine Patients (Sandimmune)
 |  | Sandimmune | Azathioprine | Kidney | Heart | Liver
Body System | Adverse Reactions | (N = 227)% | (N = 228)% | (N = 705)% | (N = 112)% | (N = 75)%
Genitourinary | Renal Dysfunction | 32 | 6 | 25 | 38 | 37
Cardiovascular | Hypertension | 26 | 18 | 13 | 53 | 27
 | Cramps | 4 | < 1 | 2 | < 1 | 0
Skin | Hirsutism | 21 | < 1 | 21 | 28 | 45
 | Acne | 6 | 8 | 2 | 2 | 1
Central Nervous System | Tremor | 12 | 0 | 21 | 31 | 55
 | Convulsions | 3 | 1 | 1 | 4 | 5
 | Headache | 2 | < 1 | 2 | 15 | 4
Gastrointestinal | Gum Hyperplasia | 4 | 0 | 9 | 5 | 16
 | Diarrhea | 3 | < 1 | 3 | 4 | 8
 | Nausea/Vomiting | 2 | < 1 | 4 | 10 | 4
 | Hepatotoxicity | < 1 | < 1 | 4 | 7 | 4
 | Abdominal Discomfort | < 1 | 0 | < 1 | 7 | 0
Autonomic Nervous System | Paresthesia | 3 | 0 | 1 | 2 | 1
 | Flushing | < 1 | 0 | 4 | 0 | 4
Hematopoietic | Leukopenia | 2 | 19 | < 1 | 6 | 0
 | Lymphoma | < 1 | 0 | 1 | 6 | 1
Respiratory | Sinusitis | < 1 | 0 | 4 | 3 | 7
Miscellaneous | Gynecomastia | < 1 | 0 | < 1 | 4 | 3

Among 705 kidney transplant patients treated with cyclosporine oral solution (Sandimmune) in clinical trials, the reason for treatment discontinuation was renal toxicity in 5.4%, infection in 0.9%, lack of efficacy in 1.4%, acute tubular necrosis in 1.0%, lymphoproliferative disorders in 0.3%, hypertension in 0.3%, and other reasons in 0.7% of the patients.

The following reactions occurred in 2% or less of cyclosporine-treated patients: allergic reactions, anemia, anorexia, confusion, conjunctivitis, edema, fever, brittle fingernails, gastritis, hearing loss, hiccups, hyperglycemia, migraine (Neoral), muscle pain, peptic ulcer, thrombocytopenia, tinnitus.

The following reactions occurred rarely: anxiety, chest pain, constipation, depression, hair breaking, hematuria, joint pain, lethargy, mouth sores, myocardial infarction, night sweats, pancreatitis, pruritus, swallowing difficulty, tingling, upper GI bleeding, visual disturbance, weakness, weight loss.

Patients receiving immunosuppressive therapies, including cyclosporine and cyclosporine-containing regimens, are at increased risk of infections (viral, bacterial, fungal, parasitic). Both generalized and localized infections can occur. Preexisting infections may also be aggravated. Fatal outcomes have been reported (see WARNINGS).

Infectious Complications in Historical Randomized Studies
in Renal Transplant Patients Using Sandimmune
 | Cyclosporine Treatment | Azathioprine with Steroids*
 | (N=227) | (N=228)
Complication | % of Complications | % of Complications
Septicemia | 5.3 | 4.8
Abscesses | 4.4 | 5.3
Systemic Fungal Infection | 2.2 | 3.9
Local Fungal Infection | 7.5 | 9.6
Cytomegalovirus | 4.8 | 12.3
Other Viral Infections | 15.9 | 18.4
Urinary Tract Infections | 21.1 | 20.2
Wound and Skin Infections | 7.0 | 10.1
Pneumonia | 6.2 | 9.2
*Some patients also received ALG.

Postmarketing Experience, Kidney, Liver and Heart Transplantation

Hepatotoxicity

Cases of hepatotoxicity and liver injury, including cholestasis, jaundice, hepatitis and liver failure; serious and/or fatal outcomes have been reported (see WARNINGS, Hepatotoxicity).

Increased Risk of Infections

Cases of JC virus-associated progressive multifocal leukoencephalopathy (PML), sometimes fatal; and polyoma virus-associated nephropathy (PVAN), especially BK virus resulting in graft loss have been reported (see WARNINGS, Polyoma Virus Infection).

Headache, Including Migraine

Cases of migraine have been reported. In some cases, patients have been unable to continue cyclosporine, however, the final decision on treatment discontinuation should be made by the treating physician following the careful assessment of benefits versus risks.

Pain of lower extremities

Isolated cases of pain of lower extremities have been reported in association with cyclosporine. Pain of lower extremities has also been noted as part of Calcineurin-Inhibitor Induced Pain Syndrome (CIPS) as described in the literature.

Rheumatoid Arthritis

The principal adverse reactions associated with the use of cyclosporine in rheumatoid arthritis are renal dysfunction (see WARNINGS), hypertension (see PRECAUTIONS), headache, gastrointestinal disturbances, and hirsutism/hypertrichosis.

In rheumatoid arthritis patients treated in clinical trials within the recommended dose range, cyclosporine therapy was discontinued in 5.3% of the patients because of hypertension and in 7% of the patients because of increased creatinine. These changes are usually reversible with timely dose decrease or drug discontinuation. The frequency and severity of serum creatinine elevations increase with dose and duration of cyclosporine therapy. These elevations are likely to become more pronounced without dose reduction or discontinuation.

The following adverse events occurred in controlled clinical trials:

Neoral/Sandimmune Rheumatoid Arthritis
Percentage of Patients with Adverse Events ≥ 3% in any Cyclosporine Treated Group
 |  | Studies | Study | Study |  | Study |  | Study |  | Studies
 |  | 651 + 652 + 2008 | 302 | 654 |  | 654 |  | 302 |  | 651 + 652 + 2008
Body | Preferred | Sandimmune† | Sandimmune | Methotrexate & Sandimmune |  | Methotrexate & Placebo |  | Neoral |  | Placebo
System | Term | (N = 269) | (N = 155) | (N = 74) |  | (N = 73) |  | (N = 143) |  | (N = 201)
Autonomic Nervous System Disorders
 | Flushing | 2% | 2% |  | 3% |  | 0% |  | 5% | 2%
Body As A Whole–General Disorders
 | Accidental Trauma | 0% | 1% |  | 10% |  | 4% |  | 4% | 0%
 | Edema NOS* | 5% | 14% |  | 12% |  | 4% |  | 10% | < 1%
 | Fatigue | 6% | 3% |  | 8% |  | 12% |  | 3% | 7%
 | Fever | 2% | 3% |  | 0% |  | 0% |  | 2% | 4%
 | Influenza-like symptoms | < 1% | 6% |  | 1% |  | 0% |  | 3% | 2%
 | Pain | 6% | 9% |  | 10% |  | 15% |  | 13% | 4%
 | Rigors | 1% | 1% |  | 4% |  | 0% |  | 3% | 1%
Cardiovascular Disorders
 | Arrhythmia | 2% | 5% |  | 5% |  | 6% |  | 2% | 1%
 | Chest Pain | 4% | 5% |  | 1% |  | 1% |  | 6% | 1%
 | Hypertension | 8% | 26% |  | 16% |  | 12% |  | 25% | 2%
Central and Peripheral Nervous System Disorders
 | Dizziness | 8% | 6% |  | 7% |  | 3% |  | 8% | 3%
 | Headache | 17% | 23% |  | 22% |  | 11% |  | 25% | 9%
 | Migraine | 2% | 3% |  | 0% |  | 0% |  | 3% | 1%
 | Paresthesia | 8% | 7% |  | 8% |  | 4% |  | 11% | 1%
 | Tremor | 8% | 7% |  | 7% |  | 3% |  | 13% | 4%
Gastrointestinal System Disorders
 | Abdominal Pain | 15% | 15% |  | 15% |  | 7% |  | 15% | 10%
 | Anorexia | 3% | 3% |  | 1% |  | 0% |  | 3% | 3%
 | Diarrhea | 12% | 12% |  | 18% |  | 15% |  | 13% | 8%
 | Dyspepsia | 12% | 12% |  | 10% |  | 8% |  | 8% | 4%
 | Flatulence | 5% | 5% |  | 5% |  | 4% |  | 4% | 1%
 | Gastrointestinal Disorder NOS* | 0% | 2% |  | 1% |  | 4% |  | 4% | 0%
 | Gingivitis | 4% | 3% |  | 0% |  | 0% |  | 0% | 1%
 | Gum Hyperplasia | 2% | 4% |  | 1% |  | 3% |  | 4% | 1%
 | Nausea | 23% | 14% |  | 24% |  | 15% |  | 18% | 14%
 | Rectal Hemorrhage | 0% | 3% |  | 0% |  | 0% |  | 1% | 1%
 | Stomatitis | 7% | 5% |  | 16% |  | 12% |  | 6% | 8%
 | Vomiting | 9% | 8% |  | 14% |  | 7% |  | 6% | 5%
Hearing and Vestibular Disorders
 | Ear Disorder NOS* | 0% | 5% |  | 0% |  | 0% |  | 1% | 0%
Metabolic and Nutritional Disorders
 | Hypomagnesemia | 0% | 4% |  | 0% |  | 0% |  | 6% | 0%
Musculoskeletal System Disorders
 | Arthropathy | 0% | 5% |  | 0% |  | 1% |  | 4% | 0%
 | Leg Cramps / Involuntary Muscle Contractions | 2% | 11% |  | 11% |  | 3% |  | 12% | 1%
Psychiatric Disorders
 | Depression | 3% | 6% |  | 3% |  | 1% |  | 1% | 2%
 | Insomnia | 4% | 1% |  | 1% |  | 0% |  | 3% | 2%
Renal
 | Creatinine elevations ≥ 30% | 43% | 39% |  | 55% |  | 19% |  | 48% | 13%
 | Creatinine elevations ≥ 50% | 24% | 18% |  | 26% |  | 8% |  | 18% | 3%
Reproductive Disorders, Female
 | Leukorrhea | 1% | 0% |  | 4% |  | 0% |  | 1% | 0%
 | Menstrual Disorder | 3% | 2% |  | 1% |  | 0% |  | 1% | 1%
Respiratory System Disorders
 | Bronchitis | 1% | 3% |  | 1% |  | 0% |  | 1% | 3%
 | Coughing | 5% | 3% |  | 5% |  | 7% |  | 4% | 4%
 | Dyspnea | 5% | 1% |  | 3% |  | 3% |  | 1% | 2%
 | Infection NOS* | 9% | 5% |  | 0% |  | 7% |  | 3% | 10%
 | Pharyngitis | 3% | 5% |  | 5% |  | 6% |  | 4% | 4%
 | Pneumonia | 1% | 0% |  | 4% |  | 0% |  | 1% | 1%
 | Rhinitis | 0% | 3% |  | 11% |  | 10% |  | 1% | 0%
 | Sinusitis | 4% | 4% |  | 8% |  | 4% |  | 3% | 3%
 | Upper Respiratory Tract | 0% | 14% |  | 23% |  | 15% |  | 13% | 0%
Skin and Appendages Disorders
 | Alopecia | 3% | 0% |  | 1% |  | 1% |  | 4% | 4%
 | Bullous Eruption | 1% | 0% |  | 4% |  | 1% |  | 1% | 1%
 | Hypertrichosis | 19% | 17% |  | 12% |  | 0% |  | 15% | 3%
 | Rash | 7% | 12% |  | 10% |  | 7% |  | 8% | 10%
 | Skin Ulceration | 1% | 1% |  | 3% |  | 4% |  | 0% | 2%
Urinary System Disorders
 | Dysuria | 0% | 0% |  | 11% |  | 3% |  | 1% | 2%
 | Micturition Frequency | 2% | 4% |  | 3% |  | 1% |  | 2% | 2%
 | NPN, Increased | 0% | 19% |  | 12% |  | 0% |  | 18% | 0%
 | Urinary Tract Infection | 0% | 3% |  | 5% |  | 4% |  | 3% | 0%
Vascular (Extracardiac) Disorders
 | Purpura | 3% | 4% |  | 1% |  | 1% |  | 2% | 0%
† Includes patients in 2.5 mg/kg/day dose group only. *NOS = Not Otherwise Specified.

In addition, the following adverse events have been reported in 1% to < 3% of the rheumatoid arthritis patients in the cyclosporine treatment group in controlled clinical trials.

Autonomic Nervous System: dry mouth, increased sweating

Body as a Whole: allergy, asthenia, hot flushes, malaise, overdose, procedure NOS*, tumor NOS*, weight decrease, weight increase

Cardiovascular: abnormal heart sounds, cardiac failure, myocardial infarction, peripheral ischemia

Central and Peripheral Nervous System: hypoesthesia, neuropathy, vertigo

Endocrine: goiter

Gastrointestinal: constipation, dysphagia, enanthema, eructation, esophagitis, gastric ulcer, gastritis, gastroenteritis, gingival bleeding, glossitis, peptic ulcer, salivary gland enlargement, tongue disorder, tooth disorder

Infection: abscess, bacterial infection, cellulitis, folliculitis, fungal infection, herpes simplex, herpes zoster, renal abscess, moniliasis, tonsillitis, viral infection

Hematologic: anemia, epistaxis, leukopenia, lymphadenopathy

Liver and Biliary System: bilirubinemia

Metabolic and Nutritional: diabetes mellitus, hyperkalemia, hyperuricemia, hypoglycemia

Musculoskeletal System: arthralgia, bone fracture, bursitis, joint dislocation, myalgia, stiffness, synovial cyst, tendon disorder

Neoplasms: breast fibroadenosis, carcinoma

Psychiatric: anxiety, confusion, decreased libido, emotional lability, impaired concentration, increased libido, nervousness, paroniria, somnolence

Reproductive (Female): breast pain, uterine hemorrhage

Respiratory System: abnormal chest sounds, bronchospasm

Skin and Appendages: abnormal pigmentation, angioedema, dermatitis, dry skin, eczema, nail disorder, pruritus, skin disorder, urticaria

Special Senses: abnormal vision, cataract, conjunctivitis, deafness, eye pain, taste perversion, tinnitus, vestibular disorder

Urinary System: abnormal urine, hematuria, increased BUN, micturition urgency, nocturia, polyuria, pyelonephritis, urinary incontinence

*NOS = Not Otherwise Specified.

Psoriasis

The principal adverse reactions associated with the use of cyclosporine in patients with psoriasis are renal dysfunction, headache, hypertension, hypertriglyceridemia, hirsutism/hypertrichosis, paresthesia or hyperesthesia, influenza-like symptoms, nausea/vomiting, diarrhea, abdominal discomfort, lethargy, and musculoskeletal or joint pain.

In psoriasis patients treated in US controlled clinical studies within the recommended dose range, cyclosporine therapy was discontinued in 1.0% of the patients because of hypertension and in 5.4% of the patients because of increased creatinine. In the majority of cases, these changes were reversible after dose reduction or discontinuation of cyclosporine.

There has been one reported death associated with the use of cyclosporine in psoriasis. A 27-year-old male developed renal deterioration and was continued on cyclosporine. He had progressive renal failure leading to death.

Frequency and severity of serum creatinine increases with dose and duration of cyclosporine therapy. These elevations are likely to become more pronounced and may result in irreversible renal damage without dose reduction or discontinuation.

Adverse Events Occurring in 3% or More of Psoriasis Patients in Controlled Clinical Trials
Body System* | Preferred Term | Neoral (N = 182) | Sandimmune (N = 185)
Infection or Potential Infection |  | 24.7% | 24.3%
 | Influenza-Like Symptoms | 9.9% | 8.1%
 | Upper Respiratory Tract Infections | 7.7% | 11.3%
Cardiovascular System |  | 28.0% | 25.4%
 | Hypertension** | 27.5% | 25.4%
Urinary System |  | 24.2% | 16.2%
 | Increased Creatinine | 19.8% | 15.7%
Central and Peripheral Nervous System |  | 26.4% | 20.5%
 | Headache | 15.9% | 14.0%
 | Paresthesia | 7.1% | 4.8%
Musculoskeletal System |  | 13.2% | 8.7%
 | Arthralgia | 6.0% | 1.1%
Body As a Whole–General |  | 29.1% | 22.2%
 | Pain | 4.4% | 3.2%
Metabolic and Nutritional |  | 9.3% | 9.7%
Reproductive, Female |  | 8.5% (4 of 47 females) | 11.5% (6 of 52 females)
Resistance Mechanism |  | 18.7% | 21.1%
Skin and Appendages |  | 17.6% | 15.1%
 | Hypertrichosis | 6.6% | 5.4%
Respiratory System |  | 5.0% | 6.5%
 | Bronchospasm, Coughing, Dyspnea, Rhinitis | 5.0% | 4.9%
Psychiatric |  | 5.0% | 3.8%
Gastrointestinal System |  | 19.8% | 28.7%
 | Abdominal Pain | 2.7% | 6.0%
 | Diarrhea | 5.0% | 5.9%
 | Dyspepsia | 2.2% | 3.2%
 | Gum Hyperplasia | 3.8% | 6.0%
 | Nausea | 5.5% | 5.9%
White cell and RES |  | 4.4% | 2.7%
*Total percentage of events within the system.
**Newly occurring hypertension = SBP ≥ 160 mm Hg and/or DBP ≥ 90 mm Hg.

The following events occurred in 1% to less than 3% of psoriasis patients treated with cyclosporine:

Body as a Whole: fever, flushes, hot flushes

Cardiovascular: chest pain

Central and Peripheral Nervous System: appetite increased, insomnia, dizziness, nervousness, vertigo

Gastrointestinal: abdominal distention, constipation, gingival bleeding

Liver and Biliary System: hyperbilirubinemia

Neoplasms: skin malignancies [squamous cell (0.9%) and basal cell (0.4%) carcinomas]

Reticuloendothelial: platelet, bleeding, and clotting disorders, red blood cell disorder

Respiratory: infection, viral and other infection

Skin and Appendages: acne, folliculitis, keratosis, pruritus, rash, dry skin

Urinary System: micturition frequency

Vision: abnormal vision

Mild hypomagnesemia and hyperkalemia may occur but are asymptomatic. Increases in uric acid may occur and attacks of gout have been rarely reported. A minor and dose related hyperbilirubinemia has been observed in the absence of hepatocellular damage. Cyclosporine therapy may be associated with a modest increase of serum triglycerides or cholesterol. Elevations of triglycerides (> 750 mg/dL) occur in about 15% of psoriasis patients; elevations of cholesterol (> 300 mg/dL) are observed in less than 3% of psoriasis patients. Generally, these laboratory abnormalities are reversible upon dose reduction or discontinuation of cyclosporine.

Postmarketing Experience, Psoriasis

Cases of transformation to erythrodermic psoriasis or generalized pustular psoriasis upon either withdrawal or reduction of cyclosporine in patients with chronic plaque psoriasis have been reported.

OVERDOSAGE

There is a minimal experience with cyclosporine overdosage. Forced emesis and gastric lavage can be of value up to 2 hours after administration of Neoral. Transient hepatotoxicity and nephrotoxicity may occur which should resolve following drug withdrawal. Oral doses of cyclosporine up to 10 g (about 150 mg/kg) have been tolerated with relatively minor clinical consequences, such as vomiting, drowsiness, headache, tachycardia and, in a few patients, moderately severe, reversible impairment of renal function. However, serious symptoms of intoxication have been reported following accidental parenteral overdosage with cyclosporine in premature neonates. General supportive measures and symptomatic treatment should be followed in all cases of overdosage. Cyclosporine is not dialyzable to any great extent, nor is it cleared well by charcoal hemoperfusion. The oral dosage at which half of experimental animals are estimated to die is 31 times, 39 times, and > 54 times the human maintenance dose for transplant patients (6mg/kg; corrections based on body surface area) in mice, rats, and rabbits.

DOSAGE AND ADMINISTRATION

Neoral Soft Gelatin Capsules (cyclosporine capsules, USP) MODIFIED and Neoral Oral Solution (cyclosporine oral solution, USP) MODIFIED

Neoral has increased bioavailability in comparison to Sandimmune. Neoral and Sandimmune are not bioequivalent and cannot be used interchangeably without physician supervision.

The daily dose of Neoral should always be given in two divided doses (BID). It is recommended that Neoral be administered on a consistent schedule with regard to time of day and relation to meals. Grapefruit and grapefruit juice affect metabolism, increasing blood concentration of cyclosporine, thus should be avoided.

Specific Populations

Renal Impairment in Kidney, Liver, and Heart Transplantation

Cyclosporine undergoes minimal renal elimination and its pharmacokinetics do not appear to be significantly altered in patients with end-stage renal disease who receive routine hemodialysis treatments (see CLINICAL PHARMACOLOGY). However, due to its nephrotoxic potential (see WARNINGS), careful monitoring of renal function is recommended; cyclosporine dosage should be reduced if indicated (see WARNINGS and PRECAUTIONS).

Renal Impairment in Rheumatoid Arthritis and Psoriasis

Patients with impaired renal function should not receive cyclosporine (see CONTRAINDICATIONS, WARNINGS and PRECAUTIONS).

Hepatic Impairment

The clearance of cyclosporine may be significantly reduced in severe liver disease patients (see CLINICAL PHARMACOLOGY). Dose reduction may be necessary in patients with severe liver impairment to maintain blood concentrations within the recommended target range (see WARNINGS and PRECAUTIONS).

Newly Transplanted Patients

The initial oral dose of Neoral can be given 4 to 12 hours prior to transplantation or be given postoperatively. The initial dose of Neoral varies depending on the transplanted organ and the other immunosuppressive agents included in the immunosuppressive protocol. In newly transplanted patients, the initial oral dose of Neoral is the same as the initial oral dose of Sandimmune. Suggested initial doses are available from the results of a 1994 survey of the use of Sandimmune in US transplant centers. The mean ± SD initial doses were 9 ± 3 mg/kg/day for renal transplant patients (75 centers), 8 ± 4 mg/kg/day for liver transplant patients (30 centers), and 7 ± 3 mg/kg/day for heart transplant patients (24 centers). Total daily doses were divided into two equal daily doses. The Neoral dose is subsequently adjusted to achieve a pre-defined cyclosporine blood concentration (see Blood Concentration Monitoring in Transplant Patients, below). If cyclosporine trough blood concentrations are used, the target range is the same for Neoral as for Sandimmune. Using the same trough concentration target range for Neoral as for Sandimmune results in greater cyclosporine exposure when Neoral is administered (see Pharmacokinetics, Absorption). Dosing should be titrated based on clinical assessments of rejection and tolerability. Lower Neoral doses may be sufficient as maintenance therapy.

Adjunct therapy with adrenal corticosteroids is recommended initially. Different tapering dosage schedules of prednisone appear to achieve similar results. A representative dosage schedule based on the patient’s weight started with 2.0 mg/kg/day for the first 4 days tapered to 1.0 mg/kg/day by 1 week, 0.6 mg/kg/day by 2 weeks, 0.3 mg/kg/day by 1 month, and 0.15 mg/kg/day by 2 months and thereafter as a maintenance dose. Steroid doses may be further tapered on an individualized basis depending on status of patient and function of graft. Adjustments in dosage of prednisone must be made according to the clinical situation.

Conversion from Sandimmune to Neoral in Transplant Patients

In transplanted patients who are considered for conversion to Neoral from Sandimmune, Neoral should be started with the same daily dose as was previously used with Sandimmune (1:1 dose conversion). The Neoral dose should subsequently be adjusted to attain the pre-conversion cyclosporine blood trough concentration. Using the same trough concentration target range for Neoral as for Sandimmune results in greater cyclosporine exposure when Neoral is administered (see Pharmacokinetics, Absorption). Patients with suspected poor absorption of Sandimmune require different dosing strategies (see Transplant Patients with Poor Absorption of Sandimmune, below). In some patients, the increase in blood trough concentration is more pronounced and may be of clinical significance.

Until the blood trough concentration attains the pre-conversion value, it is strongly recommended that the cyclosporine blood trough concentration be monitored every 4 to 7 days after conversion to Neoral. In addition, clinical safety parameters, such as serum creatinine and blood pressure, should be monitored every two weeks during the first two months after conversion. If the blood trough concentrations are outside the desired range and/or if the clinical safety parameters worsen, the dosage of Neoral must be adjusted accordingly.

Transplant Patients with Poor Absorption of Sandimmune

Patients with lower than expected cyclosporine blood trough concentrations in relation to the oral dose of Sandimmune may have poor or inconsistent absorption of cyclosporine from Sandimmune. After conversion to Neoral, patients tend to have higher cyclosporine concentrations. Due to the increase in bioavailability of cyclosporine following conversion to Neoral, the cyclosporine blood trough concentration may exceed the target range. Particular caution should be exercised when converting patients to Neoral at doses greater than 10 mg/kg/day. The dose of Neoral should be titrated individually based on cyclosporine trough concentrations, tolerability, and clinical response. In this population the cyclosporine blood trough concentration should be measured more frequently, at least twice a week (daily, if initial dose exceeds 10 mg/kg/day) until the concentration stabilizes within the desired range.

Rheumatoid Arthritis

The initial dose of Neoral is 2.5 mg/kg/day, taken twice daily as a divided (BID) oral dose. Salicylates, NSAIDs, and oral corticosteroids may be continued (see WARNINGS and PRECAUTIONS, Drug Interactions). Onset of action generally occurs between 4 and 8 weeks. If insufficient clinical benefit is seen and tolerability is good (including serum creatinine less than 30% above baseline), the dose may be increased by 0.5 to 0.75 mg/kg/day after 8 weeks and again after 12 weeks to a maximum of 4 mg/kg/day. If no benefit is seen by 16 weeks of therapy, Neoral therapy should be discontinued.

Dose decreases by 25% to 50% should be made at any time to control adverse events, e.g., hypertension elevations in serum creatinine (30% above patient’s pretreatment level) or clinically significant laboratory abnormalities (see WARNINGS and PRECAUTIONS).

If dose reduction is not effective in controlling abnormalities or if the adverse event or abnormality is severe, Neoral should be discontinued. The same initial dose and dosage range should be used if Neoral is combined with the recommended dose of methotrexate. Most patients can be treated with Neoral doses of 3 mg/kg/day or below when combined with methotrexate doses of up to 15 mg/week (see CLINICAL PHARMACOLOGY, Clinical Trials).

There is limited long-term treatment data. Recurrence of rheumatoid arthritis disease activity is generally apparent within 4 weeks after stopping cyclosporine.

Psoriasis

The initial dose of Neoral should be 2.5 mg/kg/day. Neoral should be taken twice daily, as a divided (1.25 mg/kg BID) oral dose. Patients should be kept at that dose for at least 4 weeks, barring adverse events. If significant clinical improvement has not occurred in patients by that time, the patient’s dosage should be increased at 2-week intervals. Based on patient response, dose increases of approximately 0.5 mg/kg/day should be made to a maximum of 4.0 mg/kg/day.

Dose decreases by 25% to 50% should be made at any time to control adverse events, e.g., hypertension, elevations in serum creatinine (≥ 25% above the patient’s pretreatment level), or clinically significant laboratory abnormalities. If dose reduction is not effective in controlling abnormalities, or if the adverse event or abnormality is severe, Neoral should be discontinued (see Special Monitoring of Psoriasis Patients).

Patients generally show some improvement in the clinical manifestations of psoriasis in 2 weeks. Satisfactory control and stabilization of the disease may take 12 to 16 weeks to achieve. Results of a dose-titration clinical trial with Neoral indicate that an improvement of psoriasis by 75% or more (based on PASI) was achieved in 51% of the patients after 8 weeks and in 79% of the patients after 16 weeks. Treatment should be discontinued if satisfactory response cannot be achieved after 6 weeks at 4 mg/kg/day or the patient’s maximum tolerated dose. Once a patient is adequately controlled and appears stable the dose of Neoral should be lowered, and the patient treated with the lowest dose that maintains an adequate response (this should not necessarily be total clearing of the patient). In clinical trials, cyclosporine doses at the lower end of the recommended dosage range were effective in maintaining a satisfactory response in 60% of the patients. Doses below 2.5 mg/kg/day may also be equally effective.

Upon stopping treatment with cyclosporine, relapse will occur in approximately 6 weeks (50% of the patients) to 16 weeks (75% of the patients). In the majority of patients rebound does not occur after cessation of treatment with cyclosporine. Thirteen cases of transformation of chronic plaque psoriasis to more severe forms of psoriasis have been reported. There were 9 cases of pustular and 4 cases of erythrodermic psoriasis. Long term experience with Neoral in psoriasis patients is limited and continuous treatment for extended periods greater than one year is not recommended. Alternation with other forms of treatment should be considered in the long-term management of patients with this lifelong disease.

Neoral Oral Solution (cyclosporine oral solution, USP) MODIFIED–Recommendations for Administration

To make Neoral Oral Solution (cyclosporine oral solution, USP) MODIFIED more palatable, it should be diluted with orange or apple juice that is at room temperature. Patients should avoid switching diluents frequently. Grapefruit juice affects metabolism of cyclosporine and should be avoided. The combination of Neoral solution with milk can be unpalatable. The effect of milk on the bioavailability of cyclosporine when administered as Neoral Oral Solution has not been evaluated.

Take the prescribed amount of Neoral Oral Solution (cyclosporine oral solution, USP) MODIFIED from the container using the dosing syringe supplied, after removal of the protective cover, and transfer the solution to a glass of orange or apple juice. Stir well and drink at once. Do not allow diluted oral solution to stand before drinking. Use a glass container (not plastic). Rinse the glass with more diluent to ensure that the total dose is consumed. After use, dry the outside of the dosing syringe with a clean towel and replace the protective cover. Do not rinse the dosing syringe with water or other cleaning agents. If the syringe requires cleaning, it must be completely dry before resuming use.

Blood Concentration Monitoring in Transplant Patients

Transplant centers have found blood concentration monitoring of cyclosporine to be an essential component of patient management. Of importance to blood concentration analysis are the type of assay used, the transplanted organ, and other immunosuppressant agents being administered. While no fixed relationship has been established, blood concentration monitoring may assist in the clinical evaluation of rejection and toxicity, dose adjustments, and the assessment of compliance.

Various assays have been used to measure blood concentrations of cyclosporine. Older studies using a nonspecific assay often cited concentrations that were roughly twice those of the specific assays. Therefore, comparison between concentrations in the published literature and an individual patient concentration using current assays must be made with detailed knowledge of the assay methods employed. Current assay results are also not interchangeable and their use should be guided by their approved labeling. A discussion of the different assay methods is contained in Annals of Clinical Biochemistry 1994; 31:420-446. While several assays and assay matrices are available, there is a consensus that parent-compound-specific assays correlate best with clinical events. Of these, HPLC is the standard reference, but the monoclonal antibody RIAs and the monoclonal antibody FPIA offer sensitivity, reproducibility, and convenience. Most clinicians base their monitoring on trough cyclosporine concentrations. Applied Pharmacokinetics, Principles of Therapeutic Drug Monitoring (1992) contains a broad discussion of cyclosporine pharmacokinetics and drug monitoring techniques. Blood concentration monitoring is not a replacement for renal function monitoring or tissue biopsies.

HOW SUPPLIED

Neoral® Soft Gelatin Capsules (cyclosporine capsules, USP) MODIFIED

25 mg

Oval, blue-gray imprinted in red, “Neoral” over “25 mg.”

Packages of 30 unit-dose blisters (NDC 0078-0246-15).

100 mg

Oblong, blue-gray imprinted in red, “NEORAL” over “100 mg.”

Packages of 30 unit-dose blisters (NDC 0078-0248-15).

Store and Dispense

In the original unit-dose container at controlled room temperature 68°F to 77°F (20°C to 25°C).

Neoral® Oral Solution (cyclosporine oral solution, USP) MODIFIED

A clear, yellow liquid supplied in 50 mL bottles containing 100 mg/mL (NDC 0078-0274-22).

Store and Dispense

In the original container at controlled room temperature 68°F to 77°F (20° to 25°C). Do not store in the refrigerator. Once opened, the contents must be used within two months. At temperatures below 68°F (20°C) the solution may gel; light flocculation or the formation of a light sediment may also occur. There is no impact on product performance or dosing using the syringe provided. Allow to warm to room temperature 77°F (25°C) to reverse these changes.

Neoral® Soft Gelatin Capsules (cyclosporine capsules, USP) MODIFIED

Neoral® Oral Solution (cyclosporine oral solution, USP) MODIFIED

Distributed by:

Novartis Pharmaceuticals Corporation, East Hanover, New Jersey 07936

© Novartis

Revised: September 2023

T2023-70

PRINCIPAL DISPLAY PANEL

NOVARTIS

NDC 0078-0246-15

NEORAL® Soft Gelatin Capsules

(cyclosporine capsules, USP) MODIFIED

WARNING: Neoral® (cyclosporine capsules, USP) MODIFIED is NOT BIOEQUIVALENT to
Sandimmune® (cyclosporine capsules, USP). Do NOT use interchangeably without a
physician’s supervision.

Rx only

Novartis Pharmaceuticals Corporation, East Hanover, New Jersey 07936

30 Soft Gelatin Capsules

25 mg

PRINCIPAL DISPLAY PANEL

NOVARTIS

NDC 0078-0248-15

NEORAL® Soft Gelatin Capsules

(cyclosporine capsules, USP) MODIFIED

WARNING: Neoral® (cyclosporine capsules, USP) MODIFIED is NOT BIOEQUIVALENT to
Sandimmune® (cyclosporine capsules, USP). Do NOT use interchangeably without a
physician’s supervision.

Rx only

Novartis Pharmaceuticals Corporation, East Hanover, New Jersey 07936

30 Soft Gelatin Capsules

100 mg

PRINCIPAL DISPLAY PANEL

NOVARTIS

50 mL Size

NDC 0078-0274-22

NEORAL® Oral Solution

(cyclosporine oral solution, USP) MODIFIED

WARNING: Neoral® (cyclosporine oral solution, USP) MODIFIED is NOT

BIOEQUIVALINET to Sandimmune® (cyclosporine oral solutions, USP).

Do NOT use interchangeably without a Physician's supervision.

Each mL contains:

cyclosporine, USP 100 mg

alcohol, USP dehydrated 11.9% v/v (9.5% wt/vol.)

Rx only

Novartis Pharmaceuticals Corporation

East Hanover, New Jersey 07936

100 mg/mL